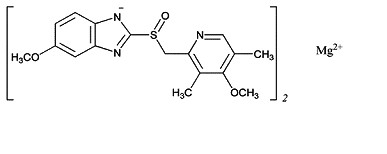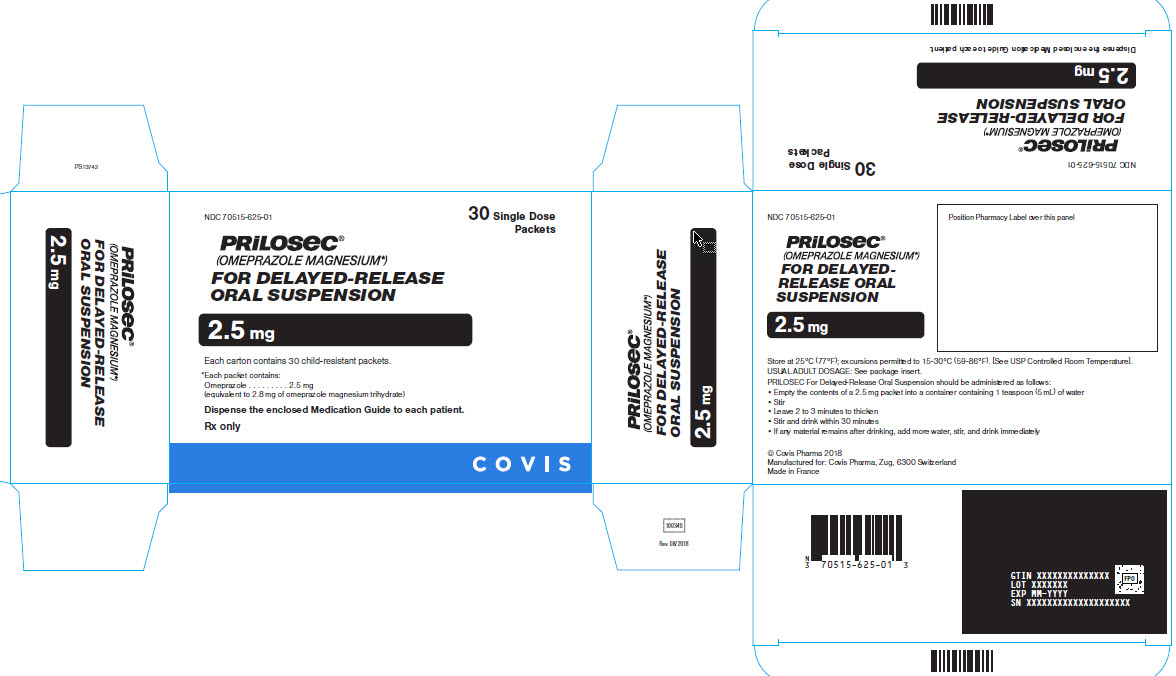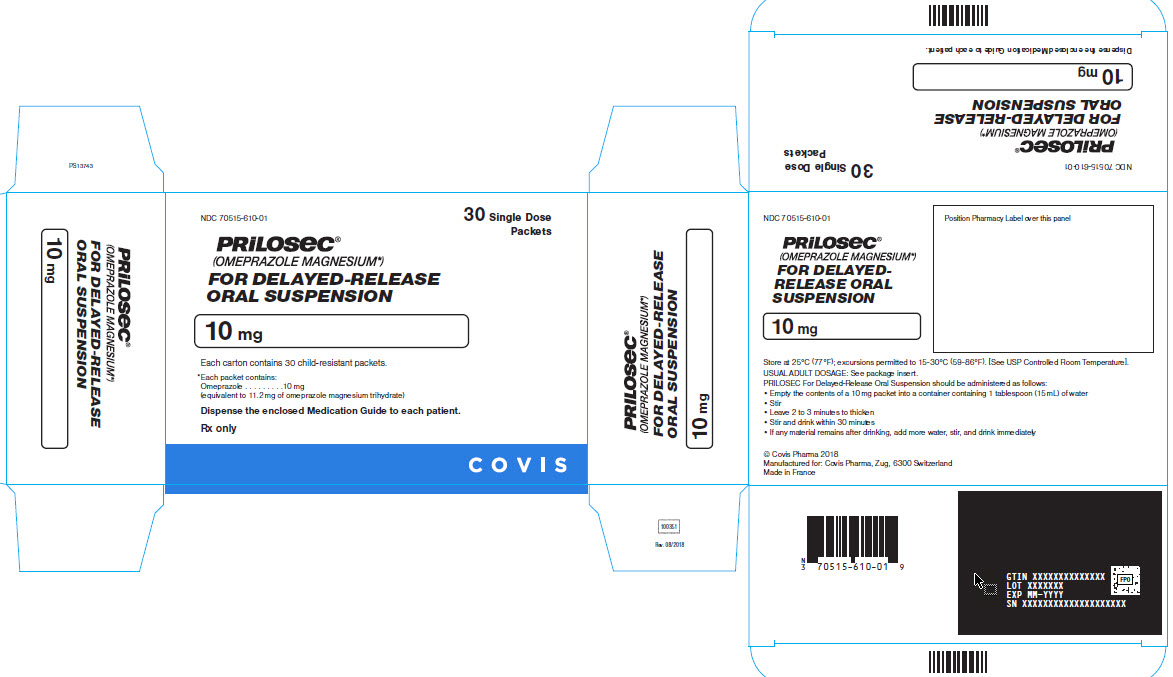 DRUG LABEL: Prilosec
NDC: 70515-625 | Form: GRANULE, DELAYED RELEASE
Manufacturer: Covis Pharma US, Inc
Category: prescription | Type: HUMAN PRESCRIPTION DRUG LABEL
Date: 20240319

ACTIVE INGREDIENTS: OMEPRAZOLE MAGNESIUM 2.5 mg/1 1
INACTIVE INGREDIENTS: GLYCERYL MONOSTEARATE; HYDROXYPROPYL CELLULOSE (1600000 WAMW); HYPROMELLOSE, UNSPECIFIED; MAGNESIUM STEARATE; METHACRYLIC ACID - ETHYL ACRYLATE COPOLYMER (1:1) TYPE A; POLYSORBATE 80; TALC; TRIETHYL CITRATE; XANTHAN GUM; CITRIC ACID MONOHYDRATE; DEXTROSE, UNSPECIFIED FORM; CROSPOVIDONE; FERRIC OXIDE RED

HIGHLIGHTS OF PRESCRIBING INFORMATION

These highlights do not include all the information needed to use PRILOSEC safely and effectively. See full prescribing information for PRILOSEC.
PRILOSEC® (omeprazole magnesium) for delayed-release oral suspension
Initial U.S. Approval: 1989

1 INDICATIONS AND USAGE

PRILOSEC is a proton pump inhibitor (PPI) indicated for the:

- Treatment of active duodenal ulcer in adults (1.1)
- Eradication of Helicobacter pylori to reduce the risk of duodenal ulcer recurrence in adults (1.2)
- Treatment of active benign gastric ulcer in adults (1.3)
- Treatment of symptomatic gastroesophageal reflux disease (GERD) in patients 1 year of age and older (1.4)
- Treatment of erosive esophagitis (EE) due to acid-mediated GERD in patients 1 month of age and older (1.5)
- Maintenance of healing of EE due to acid-mediated GERD in patients 1 year of age and older (1.6)
- Pathologic hypersecretory conditions in adults (1.7)

2 DOSAGE AND ADMINISTRATION

Indication | Recommended Adult (2.1) and Pediatric Dosage (2.2)
Treatment of Active Duodenal Ulcer | 20 mg once daily for 4 weeks; some patients may require an additional 4 weeks (2.1)
H. pylori Eradication to Reduce the Risk of Duodenal Ulcer Recurrence
Triple Therapy:
PRILOSEC; Amoxicillin; Clarithromycin | 20 mg; 1000 mg; 500 mg | Each drug twice daily for 10 days (2.1)*
Dual Therapy:
PRILOSEC; Clarithromycin | 40 mg once daily for 14 days**; 500 mg three times daily for 14 days (2.1)
Active Benign Gastric Ulcer | 40 mg once daily for 4 to 8 weeks (2.1)
Symptomatic GERD | 20 mg once daily for up to 4 weeks (2.1); See full prescribing information for weight based dosing in pediatric patients 1 year of age and older (2.2)
EE due to Acid-Mediated GERD | 20 mg once daily for 4 to 8 weeks (2.1)***; See full prescribing information for weight based dosing in pediatric patients 1 month of age and older (2.2)
Maintenance of Healing of EE due to Acid-Mediated GERD | 20 mg once daily (2.1)****; See full prescribing information for weight based dosing in pediatric patients 1 year of age and older (2.2)
Pathological Hypersecretory Conditions | Starting dose is 60 mg once daily (varies with individual patient, see full prescribing information) as long as clinically indicated (2.1)
* if ulcer present, continue PRILOSEC 20 mg once daily for an additional 18 days.
** if ulcer present, continue PRILOSEC 20 mg once daily for an additional 14 days.
*** an additional 4 weeks of treatment may be given if no response; if recurrence additional 4 to 8 week courses may be considered.
**** studied for 12 months. Reduce the dosage to 10 mg once daily for patients with hepatic impairment (Child-Pugh Class A, B, or C) and Asian patients (8.6, 8.7)

3 DOSAGE FORMS AND STRENGTHS

PRILOSEC for delayed-release oral suspension: 2.5 mg and 10 mg omeprazole in unit dose packets (3)

4 CONTRAINDICATIONS

- Patients with known hypersensitivity to substituted benzimidazoles or any component of the formulation. (4)
- Patients receiving rilpivirine-containing products. (4, 7)
- Refer to the Contraindications section of the prescribing information for clarithromycin and amoxicillin, when administered in combination with PRILOSEC. (4)

5 WARNINGS AND PRECAUTIONS

- Gastric Malignancy: In adults, symptomatic response does not preclude the presence of gastric malignancy. Consider additional follow-up and diagnostic testing. (5.1)
- Acute Tubulointerstital Nephritis: Discontinue treatment and evaluate patients. (5.2)
- Clostridium difficile-Associated Diarrhea: PPI therapy may be associated with increased risk. (5.3)
- Bone Fracture: Long-term and multiple daily dose PPI therapy may be associated with an increased risk for osteoporosis-related fractures of the hip, wrist or spine. (5.4)
- Severe Cutaneous Adverse Reactions: Discontinue at the first signs or symptoms of severe cutaneous adverse reactions or other signs of hypersensitivity and consider further evaluation. (5.5)
- Cutaneous and Systemic Lupus Erythematosus: Mostly cutaneous; new onset or exacerbation of existing disease; discontinue PRILOSEC and refer to specialist for evaluation. (5.6)
- Interaction with Clopidogrel: Avoid concomitant use of PRILOSEC. (5.7, 7)
- Cyanocobalamin (Vitamin B-12) Deficiency: Daily long-term use (e.g., longer than 3 years) may lead to malabsorption or a deficiency of cyanocobalamin. (5.8)
- Hypomagnesemia and Mineral Metabolism: Reported rarely with prolonged treatment with PPIs. (5.9)
- Interaction with St. John’s Wort or Rifampin: Avoid concomitant use of PRILOSEC. (5.10, 7)
- Interactions with Diagnostic Investigations for Neuroendocrine Tumors: Increased Chromogranin A (CgA) levels may interfere with diagnostic investigations for neuroendocrine tumors; temporarily stop PRILOSEC at least 14 days before assessing CgA levels. (5.11, 7)
- Interaction with Methotrexate: Concomitant use with PPIs may elevate and/or prolong serum concentrations of methotrexate and/or its metabolite, possibly leading to toxicity. With high dose methotrexate administration, consider a temporary withdrawal of PRILOSEC. (5.12, 7)
- Fundic Gland Polyps: Risk increases with long-term use, especially beyond one year. Use the shortest duration of therapy. (5.13)

6 ADVERSE REACTIONS

Adults: Most common adverse reactions in adults (incidence ≥2%) are

- Headache, abdominal pain, nausea, diarrhea, vomiting, and flatulence. (6)

Pediatric patients (1 to 16 years of age):

- Safety profile similar to that in adults, except that respiratory system events and fever were the most frequently reported reactions in pediatric studies. (8.4)

To report SUSPECTED ADVERSE REACTIONS, contact Covis Pharma at 1-877-411-2510 or FDA at 1-800-FDA-1088 or www.fda.gov/medwatch.

7 DRUG INTERACTIONS

See full prescribing information for a list of clinically important drug interactions. (7)

FULL PRESCRIBING INFORMATION

1 INDICATIONS AND USAGE

1.1 Treatment of Active Duodenal Ulcer

PRILOSEC is indicated for short-term treatment of active duodenal ulcer in adults. Most patients heal within four weeks. Some patients may require an additional four weeks of therapy.

1.2 Helicobacter pylori Eradication to Reduce the Risk of Duodenal Ulcer Recurrence

Eradication of H. pylori has been shown to reduce the risk of duodenal ulcer recurrence.

Triple Therapy

PRILOSEC in combination with clarithromycin and amoxicillin, is indicated for treatment of patients with H. pylori infection and duodenal ulcer disease (active or up to 1-year history) to eradicate H. pylori in adults.

Dual Therapy

PRILOSEC in combination with clarithromycin is indicated for treatment of patients with H. pylori infection and duodenal ulcer disease to eradicate H. pylori in adults.

Among patients who fail therapy, PRILOSEC with clarithromycin is more likely to be associated with the development of clarithromycin resistance as compared with triple therapy. In patients who fail therapy, susceptibility testing should be done. If resistance to clarithromycin is demonstrated or susceptibility testing is not possible, alternative antimicrobial therapy should be instituted [see Clinical Pharmacology (12.4) and the clarithromycin prescribing information, Microbiology section].

1.3 Treatment of Active Benign Gastric Ulcer

PRILOSEC is indicated for short-term treatment (4 to 8 weeks) of active benign gastric ulcer in adults.

1.4 Treatment of Symptomatic Gastroesophageal Reflux Disease (GERD)

PRILOSEC is indicated for the treatment of heartburn and other symptoms associated with GERD for up to 4 weeks in patients 1 year of age and older.

1.5 Treatment of Erosive Esophagitis (EE) Due to Acid-Mediated GERD

Pediatric Patients 1 Year of Age to Adults

PRILOSEC is indicated for the short-term treatment (4 to 8 weeks) of EE due to acid-mediated GERD that has been diagnosed by endoscopy in patients 1 year of age and older.

The efficacy of PRILOSEC used for longer than 8 weeks in patients with EE has not been established. If a patient does not respond to 8 weeks of treatment, an additional 4 weeks of treatment may be given. If there is recurrence of EE or GERD symptoms (e.g., heartburn), additional 4 to 8 week courses of PRILOSEC may be considered.

Pediatric Patients 1 Month to Less than 1 Year of Age

PRILOSEC is indicated for the short-term treatment (up to 6 weeks) of EE due to acid-mediated GERD in pediatric patients 1 month to less than 1 year of age.

1.6 Maintenance of Healing of EE Due to Acid-Mediated GERD

PRILOSEC is indicated for the maintenance healing of EE due to acid-mediated GERD in patients 1 year of age and older.

Controlled studies do not extend beyond 12 months.

1.7 Pathological Hypersecretory Conditions

PRILOSEC is indicated for the long-term treatment of pathological hypersecretory conditions (e.g., Zollinger-Ellison syndrome, multiple endocrine adenomas and systemic mastocytosis) in adults.

2 DOSAGE AND ADMINISTRATION

2.1 Recommended Adult Dosage Regimen by Indication

Table 1 shows the recommended dosage of PRILOSEC in adult patients by indication.

Table 1: Recommended Dosage Regimen of PRILOSEC in Adults by Indication
Indication | Dosage of PRILOSEC | Treatment Duration
Treatment of Active Duodenal Ulcer | 20 mg once daily | 4 weeks [Most patients heal within 4 weeks; some patients may require an additional 4 weeks of therapy to achieve healing]
Helicobacter pylori Eradication to Reduce the Risk of Duodenal Ulcer Recurrence | Triple Therapy; PRILOSEC 20 mg; Amoxicillin 1000 mg; Clarithromycin 500 mg; Take all three drugs twice daily | 10 days; In patients with an ulcer present at the time of initiation of therapy, continue PRILOSEC 20 mg once daily for an additional 18 days for ulcer healing and symptom relief.
Helicobacter pylori Eradication to Reduce the Risk of Duodenal Ulcer Recurrence | Dual Therapy; PRILOSEC 40 mg once daily; Clarithromycin 500 mg three times daily | 14 days; In patients with an ulcer present at the time of initiation of therapy, an additional 14 days of PRILOSEC 20 mg once daily is recommended for ulcer healing and symptom relief.
Active Benign Gastric Ulcer | 40 mg once daily | 4 to 8 weeks
Treatment of Symptomatic GERD | 20 mg once daily | Up to 4 weeks
Treatment of EE due to Acid-Mediated GERD | 20 mg once daily | 4 to 8 weeks [The efficacy of PRILOSEC used for longer than 8 weeks in patients with EE has not been established. If a patient does not respond to 8 weeks of treatment, an additional 4 weeks of treatment may be given. If there is recurrence of EE or GERD symptoms (e.g., heartburn), additional 4 to 8 week courses of PRILOSEC may be considered.]
Maintenance of Healing of EE due to Acid-Mediated GERD | 20 mg once daily [Dosage reduction to 10 mg once daily is recommended for patients with hepatic impairment (Child-Pugh Class A, B or C) and Asian patients when used for the maintenance of healing of EE [see Use in Specific Populations (8.6, 8.7) and Clinical Pharmacology (12.3, 12.5)].] | Controlled studies do not extend beyond 12 months.
Pathological Hypersecretory Conditions | Starting dose is 60 mg once daily; adjust to patient needs; Daily dosages of greater than 80 mg should be administered in divided doses.; Dosages up to 120 mg three times daily have been administered. | As long as clinically indicated.; Some patients with Zollinger-Ellison syndrome have been treated continuously for more than 5 years.

2.2 Recommended Pediatric Dosage Regimen by Indication

Table 2 shows the recommended dosage of PRILOSEC in pediatric patients by indication.

Table 2: Recommended Dosage Regimen of PRILOSEC in Pediatric Patients by Indication
Indication | PRILOSEC Dosage Regimen and Duration
Indication | Patient Age | Weight-Based Dose (mg) | Regimen and Duration
Treatment of Symptomatic GERD | 1 to 16 years | 5 to less than 10 kg: 5 mg | Once daily for up to 4 weeks
Treatment of Symptomatic GERD | 1 to 16 years | 10 to less than 20 kg: 10 mg | Once daily for up to 4 weeks
Treatment of Symptomatic GERD | 1 to 16 years | 20 kg and greater: 20 mg | Once daily for up to 4 weeks
Treatment of EE due to Acid-Mediated GERD | 1 to 16 years | 5 to less than 10 kg: 5 mg | Once daily for 4 to 8 weeks [The efficacy of PRILOSEC used for longer than 8 weeks in patients with EE has not been established. If a patient does not respond to 8 weeks of treatment, an additional 4 weeks of treatment may be given. If there is recurrence of EE or GERD symptoms (e.g., heartburn), additional 4 to 8 week courses of PRILOSEC may be considered.]
Treatment of EE due to Acid-Mediated GERD | 1 to 16 years | 10 to less than 20 kg: 10 mg | Once daily for 4 to 8 weeks [The efficacy of PRILOSEC used for longer than 8 weeks in patients with EE has not been established. If a patient does not respond to 8 weeks of treatment, an additional 4 weeks of treatment may be given. If there is recurrence of EE or GERD symptoms (e.g., heartburn), additional 4 to 8 week courses of PRILOSEC may be considered.]
Treatment of EE due to Acid-Mediated GERD | 1 to 16 years | 20 kg and greater: 20 mg | Once daily for 4 to 8 weeks [The efficacy of PRILOSEC used for longer than 8 weeks in patients with EE has not been established. If a patient does not respond to 8 weeks of treatment, an additional 4 weeks of treatment may be given. If there is recurrence of EE or GERD symptoms (e.g., heartburn), additional 4 to 8 week courses of PRILOSEC may be considered.]
Treatment of EE due to Acid-Mediated GERD | 1 month to less than 1 year | 3 to less than 5 kg: 2.5 mg | Once daily up to 6 weeks
Treatment of EE due to Acid-Mediated GERD | 1 month to less than 1 year | 5 to less than 10 kg: 5 mg | Once daily up to 6 weeks
Treatment of EE due to Acid-Mediated GERD | 1 month to less than 1 year | 10 kg and greater: 10 mg | Once daily up to 6 weeks
Maintenance of Healing of EE due to Acid-Mediated GERD | 1 to 16 years | 5 to less than 10 kg: 5 mg | Once daily. Controlled studies do not extend beyond 12 months
Maintenance of Healing of EE due to Acid-Mediated GERD | 1 to 16 years | 10 to less than 20 kg: 10 mg | Once daily. Controlled studies do not extend beyond 12 months
Maintenance of Healing of EE due to Acid-Mediated GERD | 1 to 16 years | 20 kg and greater: 20 mg | Once daily. Controlled studies do not extend beyond 12 months

2.3 Administration Instructions

- PRILOSEC is intended to be prepared in water and administered orally or via a nasogastric (NG) or gastric tube.
- Take PRILOSEC before meals.
- Antacids may be used concomitantly with PRILOSEC.
- Missed doses: If a dose is missed, administer as soon as possible. However, if the next scheduled dose is due, do not take the missed dose, and take the next dose on time. Do not take two doses at one time to make up for a missed dose.

Oral Administration in Water

1. Empty the contents of a 2.5 mg packet into a container containing 5 mL of water.
2. Empty the contents of a 10 mg packet into a container containing 15 mL of water.
3. Stir.
4. Leave 2 to 3 minutes to thicken.
5. Stir and drink within 30 minutes.
6. If any material remains after drinking, add more water, stir and drink immediately.

Administration with Water via a NG or Gastric Tube (Size 6 or Larger)

1. Add 5 mL of water to a catheter tipped syringe and then add the contents of a 2.5 mg packet (or 15 mL of water for the 10 mg packet). It is important to only use a catheter tipped syringe when administering through a nasogastric tube or gastric tube.
2. Immediately shake the syringe and leave 2 to 3 minutes to thicken.
3. Shake the syringe and inject through the nasogastric or gastric tube into the stomach within 30 minutes.
4. Refill the syringe with an equal amount of water.
5. Shake and flush any remaining contents from the nasogastric or gastric tube into the stomach.

3 DOSAGE FORMS AND STRENGTHS

PRILOSEC For Delayed-Release Oral Suspension: 2.5 mg and 10 mg omeprazole in unit dose packets containing a fine yellow powder, consisting of white to brownish omeprazole magnesium granules and pale yellow inactive granules.

4 CONTRAINDICATIONS

- PRILOSEC is contraindicated in patients with known hypersensitivity to substituted benzimidazoles or to any component of the formulation. Hypersensitivity reactions may include anaphylaxis, anaphylactic shock, angioedema, bronchospasm, acute tubulointerstitial nephritis, and urticaria [see Warnings and Precautions (5.2), Adverse Reactions (6)].
- Proton pump inhibitors (PPIs), including PRILOSEC, are contraindicated in patients receiving rilpivirine-containing products [see Drug Interactions (7)].
- For information about contraindications of antibacterial agents (clarithromycin and amoxicillin) indicated in combination with PRILOSEC, refer to the CONTRAINDICATIONS section of their package inserts.

5 WARNINGS AND PRECAUTIONS

5.1 Presence of Gastric Malignancy

In adults, symptomatic response to therapy with PRILOSEC does not preclude the presence of gastric malignancy. Consider additional follow-up and diagnostic testing in adult patients who have a suboptimal response or an early symptomatic relapse after completing treatment with a PPI. In older patients, also consider an endoscopy.

5.2 Acute Tubulointerstitial Nephritis

Acute tubulointerstitial nephritis (TIN) has been observed in patients taking PPIs and may occur at any point during PPI therapy. Patients may present with varying signs and symptoms from symptomatic hypersensitivity reactions to non-specific symptoms of decreased renal function (e.g., malaise, nausea, anorexia). In reported case series, some patients were diagnosed on biopsy and in the absence of extra-renal manifestations (e.g., fever, rash or arthralgia). Discontinue PRILOSEC and evaluate patients with suspected acute TIN [see Contraindications (4)].

5.3 Clostridium difficile-Associated Diarrhea

Published observational studies suggest that PPI therapy like PRILOSEC may be associated with an increased risk of Clostridium difficile-associated diarrhea, especially in hospitalized patients. This diagnosis should be considered for diarrhea that does not improve [see Adverse Reactions (6.2)].

Patients should use the lowest dose and shortest duration of PPI therapy appropriate to the condition being treated.

Clostridium difficile-associated diarrhea (CDAD) has been reported with use of nearly all antibacterial agents. For more information specific to antibacterial agents (clarithromycin and amoxicillin) indicated for use in combination with PRILOSEC, refer to Warnings and Precautions sections of the corresponding prescribing information.

5.4 Bone Fracture

Several published observational studies suggest that proton pump inhibitor (PPI) therapy may be associated with an increased risk for osteoporosis-related fractures of the hip, wrist, or spine. The risk of fracture was increased in patients who received high-dose, defined as multiple daily doses, and long-term PPI therapy (a year or longer). Patients should use the lowest dose and shortest duration of PPI therapy appropriate to the condition being treated. Patients at risk for osteoporosis-related fractures should be managed according to established treatment guidelines [see Dosage and Administration (2.1), Adverse Reactions (6.3)].

5.5 Severe Cutaneous Adverse Reactions

Severe cutaneous adverse reactions, including Stevens-Johnson syndrome (SJS) and toxic epidermal necrolysis (TEN), drug reaction with eosinophilia and systemic symptoms (DRESS), and acute generalized exanthematous pustulosis (AGEP) have been reported in association with the use of PPIs [see Adverse Reactions (6.2)]. Discontinue PRILOSEC at the first signs or symptoms of severe cutaneous adverse reactions or other signs of hypersensitivity and consider further evaluation.

5.6 Cutaneous and Systemic Lupus Erythematosus

Cutaneous lupus erythematosus (CLE) and systemic lupus erythematosus (SLE) have been reported in patients taking PPIs, including omeprazole. These events have occurred as both new onset and an exacerbation of existing autoimmune disease. The majority of PPI-induced lupus erythematosus cases were CLE.

The most common form of CLE reported in patients treated with PPIs was subacute CLE (SCLE) and occurred within weeks to years after continuous drug therapy in patients ranging from infants to the elderly. Generally, histological findings were observed without organ involvement.

Systemic lupus erythematosus (SLE) is less commonly reported than CLE in patients receiving PPIs. PPI associated SLE is usually milder than non-drug induced SLE. Onset of SLE typically occurred within days to years after initiating treatment primarily in patients ranging from young adults to the elderly. The majority of patients presented with rash; however, arthralgia and cytopenia were also reported.

Avoid administration of PPIs for longer than medically indicated. If signs or symptoms consistent with CLE or SLE are noted in patients receiving PRILOSEC, discontinue the drug and refer the patient to the appropriate specialist for evaluation. Most patients improve with discontinuation of the PPI alone in 4 to 12 weeks. Serological testing (e.g., ANA) may be positive and elevated serological test results may take longer to resolve than clinical manifestations.

5.7 Interaction with Clopidogrel

Avoid concomitant use of PRILOSEC with clopidogrel. Clopidogrel is a prodrug. Inhibition of platelet aggregation by clopidogrel is entirely due to an active metabolite. The metabolism of clopidogrel to its active metabolite can be impaired by use with concomitant medications, such as omeprazole, that inhibit CYP2C19 activity. Concomitant use of clopidogrel with 80 mg omeprazole reduces the pharmacological activity of clopidogrel, even when administered 12 hours apart.

When using PRILOSEC, consider alternative anti-platelet therapy [see Drug Interactions (7) and Clinical Pharmacology (12.3)].

5.8 Cyanocobalamin (Vitamin B-12) Deficiency

Daily treatment with any acid-suppressing medications over a long period of time (e.g., longer than 3 years) may lead to malabsorption of cyanocobalamin (vitamin B-12) caused by hypo- or achlorhydria. Rare reports of cyanocobalamin deficiency occurring with acid-suppressing therapy have been reported in the literature. This diagnosis should be considered if clinical symptoms consistent with cyanocobalamin deficiency are observed in patients treated with PRILOSEC.

5.9 Hypomagnesemia and Mineral Metabolism

Hypomagnesemia, symptomatic and asymptomatic, has been reported rarely in patients treated with PPIs for at least three months, in most cases after a year of therapy. Serious adverse events include tetany, arrhythmias, and seizures. Hypomagnesemia may lead to hypocalcemia and/or hypokalemia and may exacerbate underlying hypocalcemia in at-risk patients. In most patients, treatment of hypomagnesemia required magnesium replacement and discontinuation of the PPI.

For patients expected to be on prolonged treatment or who take PPIs with medications such as digoxin or drugs that may cause hypomagnesemia (e.g., diuretics), health care professionals may consider monitoring magnesium levels prior to initiation of PPI treatment and periodically [see Adverse Reactions (6.2)].

Consider monitoring magnesium and calcium levels prior to initiation of PRILOSEC and periodically while on treatment in patients with a preexisting risk of hypocalcemia (e.g., hypoparathyroidism) Supplement with magnesium and/or calcium as necessary. If hypocalcemia is refractory to treatment, consider discontinuing the PPI.

5.10 Interaction with St. John’s Wort or Rifampin

Drugs which induce CYP2C19 or CYP3A4 (such as St. John’s Wort or rifampin) can substantially decrease omeprazole concentrations [see Drug Interactions (7)]. Avoid concomitant use of PRILOSEC with St. John’s Wort or rifampin.

5.11 Interactions with Diagnostic Investigations for Neuroendocrine Tumors

Serum chromogranin A (CgA) levels increase secondary to drug-induced decreases in gastric acidity. The increased CgA level may cause false positive results in diagnostic investigations for neuroendocrine tumors. Healthcare providers should temporarily stop PRILOSEC treatment at least 14 days before assessing CgA levels and consider repeating the test if initial CgA levels are high. If serial tests are performed (e.g., for monitoring), the same commercial laboratory should be used for testing, as reference ranges between tests may vary [see Drug Interactions (7)].

5.12 Interaction with Methotrexate

Literature suggests that concomitant use of PPIs with methotrexate (primarily at high dose) may elevate and prolong serum levels of methotrexate and/or its metabolite, possibly leading to methotrexate toxicities. In high-dose methotrexate administration a temporary withdrawal of the PPI may be considered in some patients [see Drug Interactions (7)].

5.13 Fundic Gland Polyps

PPI use is associated with an increased risk of fundic gland polyps that increases with long-term use, especially beyond one year. Most PPI users who developed fundic gland polyps were asymptomatic and fundic gland polyps were identified incidentally on endoscopy. Use the shortest duration of PPI therapy appropriate to the condition being treated.

6 ADVERSE REACTIONS

The following serious adverse reactions are described below and elsewhere in labeling:

- Acute Tubulointerstitial Nephritis [see Warnings and Precautions (5.2)]
- Clostridium difficile-Associated Diarrhea [see Warnings and Precautions (5.3)]
- Bone Fracture [see Warnings and Precautions (5.4)]
- Severe Cutaneous Adverse Reactions [see Warnings and Precautions (5.5)]
- Cutaneous and Systemic Lupus Erythematosus [see Warnings and Precautions (5.6)]
- Cyanocobalamin (Vitamin B-12) Deficiency [see Warnings and Precautions (5.8)]
- Hypomagnesemia and Mineral Metabolism [see Warnings and Precautions (5.9)]
- Fundic Gland Polyps [see Warnings and Precautions (5.13)]

6.1 Clinical Trials Experience with PRILOSEC

Monotherapy

Because clinical trials are conducted under widely varying conditions, adverse reaction rates observed in the clinical trials of a drug cannot be directly compared to rates in the clinical trials of another drug and may not reflect the rates observed in practice.

The safety data described below reflect exposure to omeprazole magnesium delayed-release capsules in 3096 patients from worldwide clinical trials (465 patients from US studies and 2631 patients from international studies). Indications clinically studied in US trials included duodenal ulcer, resistant ulcer, and Zollinger-Ellison syndrome. The international clinical trials were double blind and open-label in design. The most common adverse reactions reported (i.e., with an incidence rate ≥2%) from PRILOSEC-treated patients enrolled in these studies included headache (7%), abdominal pain (5%), nausea (4%), diarrhea (4%), vomiting (3%), and flatulence (3%).

Additional adverse reactions that were reported with an incidence ≥1% included acid regurgitation (2%), upper respiratory infection (2%), constipation (2%), dizziness (2%), rash (2%), asthenia (1%), back pain (1%), and cough (1%).

The clinical trial safety profile in patients greater than 65 years of age was similar to that in patients 65 years of age or less.

The clinical trial safety profile in pediatric patients who received omeprazole magnesium delayed-release capsules was similar to that in adult patients. Unique to the pediatric population, however, adverse reactions of the respiratory system were frequently reported in the 1 month to <1 year age group, the 1 to <2 year age group, and the 2 to 16 year age group (42%, 75%, and 19%, respectively). In addition, otitis media was frequently reported in the 1 month to <1 year age group (22%), fever was frequently reported in the 1 to <2 year age group (33%), and accidental injuries were frequently reported in the 2 to 16 year age group (4%) [see Use in Specific Populations (8.4)].

6.2 Clinical Trials Experience with PRILOSEC in Combination Therapy for H. pylori Eradication

In clinical trials using either dual therapy with omeprazole magnesium delayed-release capsules and clarithromycin, or triple therapy with omeprazole magnesium delayed-release capsules, clarithromycin, and amoxicillin, no adverse reactions unique to these drug combinations were observed. Adverse reactions observed were limited to those previously reported with omeprazole, clarithromycin, or amoxicillin alone.

Dual Therapy (omeprazole magnesium delayed-release capsules/clarithromycin)

Adverse reactions observed in controlled clinical trials using combination therapy with omeprazole magnesium delayed-release capsules and clarithromycin (n = 346) that differed from those previously described for omeprazole magnesium delayed-release capsules alone were taste perversion (15%), tongue discoloration (2%), rhinitis (2%), pharyngitis (1%), and flu-syndrome (1%). (For more information on clarithromycin, refer to the clarithromycin prescribing information, Adverse Reactions section.)

Triple Therapy (omeprazole magnesium delayed-release capsules/clarithromycin/amoxicillin)

The most frequent adverse reactions observed in clinical trials using combination therapy with omeprazole magnesium delayed-release capsules, clarithromycin, and amoxicillin (n = 274) were diarrhea (14%), taste perversion (10%), and headache (7%). None of these occurred at a higher frequency than that reported by patients taking antimicrobial agents alone. (For more information on clarithromycin or amoxicillin, refer to the respective prescribing information, Adverse Reactions sections.)

6.3 Postmarketing Experience

The following adverse reactions have been identified during post-approval use of omeprazole. Because these reactions are voluntarily reported from a population of uncertain size, it is not always possible to reliably estimate their actual frequency or establish a causal relationship to drug exposure.

Body As a Whole: Hypersensitivity reactions including anaphylaxis, anaphylactic shock, angioedema, bronchospasm, interstitial nephritis, urticaria, (see also Skin below); fever; pain; fatigue; malaise; systemic lupus erythematosus

Cardiovascular: Chest pain or angina, tachycardia, bradycardia, palpitations, elevated blood pressure, peripheral edema

Endocrine: Gynecomastia

Gastrointestinal: Pancreatitis (some fatal), anorexia, irritable colon, fecal discoloration, esophageal candidiasis, mucosal atrophy of the tongue, stomatitis, abdominal swelling, dry mouth, microscopic colitis, fundic gland polyps.

Gastroduodenal carcinoids have been reported in patients with ZE syndrome on long-term treatment with omeprazole. This finding is believed to be a manifestation of the underlying condition, which is known to be associated with such tumors.

Hepatic: Liver disease including hepatic failure (some fatal), liver necrosis (some fatal), hepatic encephalopathy hepatocellular disease, cholestatic disease, mixed hepatitis, jaundice, and elevations of liver function tests [ALT, AST, GGT, alkaline phosphatase, and bilirubin]

Infections and Infestations: Clostridium difficile-associated diarrhea

Metabolism and Nutritional disorders: Hypomagnesemia, hypocalcemia, hypokalemia [Warnings and Precautions (5.9)], hyponatremia, hypoglycemia, weight gain

Musculoskeletal: Muscle weakness, myalgia, muscle cramps, joint pain, leg pain, bone fracture

Nervous System/Psychiatric: Psychiatric and sleep disturbances including depression, agitation, aggression, hallucinations, confusion, insomnia, nervousness, apathy, somnolence, anxiety, and dream abnormalities; tremors, paresthesia; vertigo

Respiratory: Epistaxis, pharyngeal pain

Skin: Severe generalized skin reactions including toxic SJS/TEN (some fatal), DRESS, AGEP, cutaneous lupus erythematosus and erythema multiforme; photosensitivity; urticaria; rash; skin inflammation; pruritus; petechiae; purpura; alopecia; dry skin; hyperhidrosis

Special Senses: Tinnitus, taste perversion

Ocular: Optic atrophy, anterior ischemic optic neuropathy, optic neuritis, dry eye syndrome, ocular irritation, blurred vision, double vision

Urogenital: Interstitial nephritis, hematuria, proteinuria, elevated serum creatinine, microscopic pyuria, urinary tract infection, glycosuria, urinary frequency, testicular pain, erectile dysfunction

Hematologic: Agranulocytosis (some fatal), hemolytic anemia, pancytopenia, neutropenia, anemia, thrombocytopenia, leukopenia, leukocytosis

7 DRUG INTERACTIONS

Table 3 and Table 4 include drugs with clinically important drug interactions and interaction with diagnostics when administered concomitantly with omeprazole and instructions for preventing or managing them.

Consult the labeling of concomitantly used drugs to obtain further information about interactions with PPIs.

Table 3: Clinically Relevant Interactions Affecting Drugs Co-Administered with Omeprazole and Interaction with Diagnostics
Antiretrovirals
Clinical Impact: | The effect of PPIs on antiretroviral drugs is variable. The clinical importance and the mechanisms behind these interactions are not always known.; - Decreased exposure of some antiretroviral drugs (e.g., rilpivirine, atazanavir and nelfinavir) when used concomitantly with omeprazole may reduce antiviral effect and promote the development of drug resistance [see Clinical Pharmacology (12.3)]. - Increased exposure of other antiretroviral drugs (e.g., saquinavir) when used concomitantly with omeprazole may increase toxicity [see Clinical Pharmacology (12.3)]. - There are other antiretroviral drugs which do not result in clinically relevant interactions with omeprazole.
Intervention: | Rilpivirine-containing products: Concomitant use with PRILOSEC is contraindicated [see Contraindications (4)].; Atazanavir: Avoid concomitant use with PRILOSEC. See prescribing information for atazanavir for dosing information.; Nelfinavir: Avoid concomitant use with PRILOSEC. See prescribing information for nelfinavir.; Saquinavir: See the prescribing information for saquinavir for monitoring of potential saquinavir-related toxicities.; Other antiretrovirals: See prescribing information for specific antiretroviral drugs.
Warfarin
Clinical Impact: | Increased INR and prothrombin time in patients receiving PPIs, including omeprazole, and warfarin concomitantly. Increases in INR and prothrombin time may lead to abnormal bleeding and even death.
Intervention: | Monitor INR and prothrombin time and adjust the dose of warfarin, if needed, to maintain target INR range.
Methotrexate
Clinical Impact: | Concomitant use of omeprazole with methotrexate (primarily at high dose) may elevate and prolong serum concentrations of methotrexate and/or its metabolite hydroxymethotrexate, possibly leading to methotrexate toxicities. No formal drug interaction studies of high-dose methotrexate with PPIs have been conducted [see Warnings and Precautions (5.11)].
Intervention: | A temporary withdrawal of PRILOSEC may be considered in some patients receiving high-dose methotrexate.
CYP2C19 Substrates (e.g., clopidogrel, citalopram, cilostazol, phenytoin, diazepam)
Clopidogrel
Clinical Impact: | Concomitant use of omeprazole 80 mg results in reduced plasma concentrations of the active metabolite of clopidogrel and a reduction in platelet inhibition [see Clinical Pharmacology (12.3)].; There are no adequate combination studies of a lower dose of omeprazole or a higher dose of clopidogrel in comparison with the approved dose of clopidogrel.
Intervention: | Avoid concomitant use with PRILOSEC. Consider use of alternative anti-platelet therapy [see Warnings and Precautions (5.6)].
Citalopram
Clinical Impact: | Increased exposure of citalopram leading to an increased risk of QT prolongation [see Clinical Pharmacology (12.3)].
Intervention: | Limit the dose of citalopram to a maximum of 20 mg per day. See prescribing information for citalopram.
Cilostazol
Clinical Impact: | Increased exposure of one of the active metabolites of cilostazol (3,4-dihydro-cilostazol) [see Clinical Pharmacology (12.3)].
Intervention: | Reduce the dose of cilostazol to 50 mg twice daily. See prescribing information for cilostazol.
Phenytoin
Clinical Impact: | Potential for increased exposure of phenytoin.
Intervention: | Monitor phenytoin serum concentrations. Dose adjustment may be needed to maintain therapeutic drug concentrations. See prescribing information for phenytoin.
Diazepam
Clinical Impact: | Increased exposure of diazepam [see Clinical Pharmacology (12.3)].
Intervention: | Monitor patients for increased sedation and reduce the dose of diazepam as needed.
Digoxin
Clinical Impact: | Potential for increased exposure of digoxin [see Clinical Pharmacology (12.3)].
Intervention: | Monitor digoxin concentrations. Dose adjustment may be needed to maintain therapeutic drug concentrations. See digoxin prescribing information.
Drugs Dependent on Gastric pH for Absorption
(e.g., iron salts, erlotinib, dasatinib, nilotinib, mycophenolate mofetil, ketoconazole/itraconazole)
Clinical Impact: | Omeprazole can reduce the absorption of other drugs due to its effect on reducing intragastric acidity.
Intervention: | Mycophenolate mofetil (MMF): Co-administration of omeprazole in healthy subjects and in transplant patients receiving MMF has been reported to reduce the exposure to the active metabolite, mycophenolic acid (MPA), possibly due to a decrease in MMF solubility at an increased gastric pH. The clinical relevance of reduced MPA exposure on organ rejection has not been established in transplant patients receiving PRILOSEC and MMF. Use PRILOSEC with caution in transplant patients receiving MMF [see Clinical Pharmacology (12.3)].; See the prescribing information for other drugs dependent on gastric pH for absorption.
Combination Therapy with Clarithromycin and Amoxicillin
Clinical Impact: | Concomitant administration of clarithromycin with other drugs can lead to serious adverse reactions, including potentially fatal arrhythmias, and are contraindicated.; Amoxicillin also has drug interactions.
Intervention: | See Contraindications, Warnings and Precautions in prescribing information for clarithromycin.; See Drug Interactions in prescribing information for amoxicillin.
Tacrolimus
Clinical Impact: | Potential for increased exposure of tacrolimus, especially in transplant patients who are intermediate or poor metabolizers of CYP2C19.
Intervention: | Monitor tacrolimus whole blood concentrations. Dose adjustment may be needed to maintain therapeutic drug concentrations. See prescribing information for tacrolimus.
Interactions with Investigations of Neuroendocrine Tumors
Clinical Impact: | Serum chromogranin A (CgA) levels increase secondary to PPI-induced decreases in gastric acidity. The increased CgA level may cause false positive results in diagnostic investigations for neuroendocrine tumors [see Warnings and Precautions (5.10), Clinical Pharmacology (12.2)].
Intervention: | Temporarily stop PRILOSEC treatment at least 14 days before assessing CgA levels and consider repeating the test if initial CgA levels are high. If serial tests are performed (e.g., for monitoring), the same commercial laboratory should be used for testing, as reference ranges between tests may vary.
Interaction with Secretin Stimulation Test
Clinical Impact: | Hyper-response in gastrin secretion in response to secretin stimulation test, falsely suggesting gastrinoma.
Intervention: | Temporarily stop PRILOSEC treatment at least 14 days before assessing to allow gastrin levels to return to baseline [see Clinical Pharmacology (12.2)].
False Positive Urine Tests for THC
Clinical Impact: | There have been reports of false positive urine screening tests for tetrahydrocannabinol (THC) in patients receiving PPIs.
Intervention: | An alternative confirmatory method should be considered to verify positive results.
Other
Clinical Impact: | There have been clinical reports of interactions with other drugs metabolized via the cytochrome P450 system (e.g., cyclosporine, disulfiram).
Intervention: | Monitor patients to determine if it is necessary to adjust the dosage of these other drugs when taken concomitantly with PRILOSEC.

Table 4: Clinically Relevant Interactions Affecting Omeprazole When Co-Administered with Other Drugs
CYP2C19 or CYP3A4 Inducers
Clinical Impact: | Decreased exposure of omeprazole when used concomitantly with strong inducers [see Clinical Pharmacology (12.3)].
Intervention: | St. John’s Wort, rifampin: Avoid concomitant use with PRILOSEC [see Warnings and Precautions (5.9)].; Ritonavir-containing products: see prescribing information for specific drugs.
CYP2C19 or CYP3A4 Inhibitors
Clinical Impact: | Increased exposure of omeprazole [see Clinical Pharmacology (12.3)].
Intervention: | Voriconazole: Dose adjustment of PRILOSEC is not normally required. However, in patients with Zollinger-Ellison syndrome, who may require higher doses, dose adjustment may be considered.; See prescribing information for voriconazole.

8 USE IN SPECIFIC POPULATIONS

8.1 Pregnancy

Risk Summary

There are no adequate and well-controlled studies with omeprazole in pregnant women. Available epidemiologic data fail to demonstrate an increased risk of major congenital malformations or other adverse pregnancy outcomes with first trimester omeprazole use. Reproduction studies in rats and rabbits resulted in dose-dependent embryo-lethality at omeprazole doses that were approximately 3.4 to 34 times an oral human dose of 40 mg (based on a body surface area for a 60 kg person).

Teratogenicity was not observed in animal reproduction studies with administration of oral esomeprazole (an enantiomer of omeprazole) magnesium in rats and rabbits during organogenesis with doses about 68 times and 42 times, respectively, an oral human dose of 40 mg esomeprazole or 40 mg omeprazole (based on body surface area for a 60 kg person). Changes in bone morphology were observed in offspring of rats dosed through most of pregnancy and lactation at doses equal to or greater than approximately 34 times an oral human dose of 40 mg esomeprazole or 40 mg omeprazole. When maternal administration was confined to gestation only, there were no effects on bone physeal morphology in the offspring at any age [see Data].

The estimated background risks of major birth defects and miscarriage for the indicated population are unknown. All pregnancies have a background risk of birth defect, loss or other adverse outcomes. In the US general population, the estimated background risk of major birth defects and miscarriage in clinically recognized pregnancies is 2% to 4% and 15% to 20%, respectively.

Data

Human Data

Four published epidemiological studies compared the frequency of congenital abnormalities among infants born to women who used omeprazole during pregnancy with the frequency of abnormalities among infants of women exposed to H2-receptor antagonists or other controls.

A population-based retrospective cohort epidemiological study from the Swedish Medical Birth Registry, covering approximately 99% of pregnancies, from 1995 to 99, reported on 955 infants (824 exposed during the first trimester with 39 of these exposed beyond first trimester, and 131 exposed after the first trimester) whose mothers used omeprazole during pregnancy. The number of infants exposed in utero to omeprazole that had any malformation, low birth weight, low Apgar score, or hospitalization was similar to the number observed in this population. The number of infants born with ventricular septal defects and the number of stillborn infants was slightly higher in the omeprazole-exposed infants than the expected number in this population.

A population-based retrospective cohort study covering all live births in Denmark from 1996 to 2009, reported on 1,800 live births whose mothers used omeprazole during the first trimester of pregnancy and 837,317 live births whose mothers did not use any proton pump inhibitor. The overall rate of birth defects in infants born to mothers with first trimester exposure to omeprazole was 2.9% and 2.6% in infants born to mothers not exposed to any proton pump inhibitor during the first trimester.

A retrospective cohort study reported on 689 pregnant women exposed to either H2-blockers or omeprazole in the first trimester (134 exposed to omeprazole) and 1,572 pregnant women unexposed to either during the first trimester. The overall malformation rate in offspring born to mothers with first trimester exposure to omeprazole, an H2-blocker, or were unexposed was 3.6%, 5.5%, and 4.1% respectively.

A small prospective observational cohort study followed 113 women exposed to omeprazole during pregnancy (89% with first trimester exposures). The reported rate of major congenital malformations was 4% in the omeprazole group, 2% in controls exposed to non-teratogens, and 2.8% in disease-paired controls. Rates of spontaneous and elective abortions, preterm deliveries, gestational age at delivery, and mean birth weight were similar among the groups.

Several studies have reported no apparent adverse short-term effects on the infant when single dose oral or intravenous omeprazole was administered to over 200 pregnant women as premedication for cesarean section under general anesthesia.

Animal Data

Omeprazole

Reproductive studies conducted with omeprazole in rats at oral doses up to 138 mg/kg/day (about 34 times an oral human dose of 40 mg on a body surface area basis) and in rabbits at doses up to 69.1 mg/kg/day (about 34 times an oral human dose of 40 mg on a body surface area basis) during organogenesis did not disclose any evidence for a teratogenic potential of omeprazole. In rabbits, omeprazole in a dose range of 6.9 to 69.1 mg/kg/day (about 3.4 to 34 times an oral human dose of 40 mg on a body surface area basis) administered during organogenesis produced dose-related increases in embryo-lethality, fetal resorptions, and pregnancy disruptions. In rats, dose-related embryo/fetal toxicity and postnatal developmental toxicity were observed in offspring resulting from parents treated with omeprazole at 13.8 to 138.0 mg/kg/day (about 3.4 to 34 times an oral human doses of 40 mg on a body surface area basis), administered prior to mating through the lactation period.

Esomeprazole

The data described below was generated from studies using esomeprazole, an enantiomer of omeprazole. The animal to human dose multiples are based on the assumption of equal systemic exposure to esomeprazole in humans following oral administration of either 40 mg esomeprazole or 40 mg omeprazole.

No effects on embryo-fetal development were observed in reproduction studies with esomeprazole magnesium in rats at oral doses up to 280 mg/kg/day (about 68 times an oral human dose of 40 mg on a body surface area basis) or in rabbits at oral doses up to 86 mg/kg/day (about 42 times an oral human dose of 40 mg esomeprazole or 40 mg omeprazole on a body surface area basis) administered during organogenesis.

A pre- and postnatal developmental toxicity study in rats with additional endpoints to evaluate bone development was performed with esomeprazole magnesium at oral doses of 14 to 280 mg/kg/day (about 3.4 to 68 times an oral human dose of 40 mg esomeprazole or 40 mg omeprazole on a body surface area basis). Neonatal/early postnatal (birth to weaning) survival was decreased at doses equal to or greater than 138 mg/kg/day (about 34 times an oral human dose of 40 mg esomeprazole or 40 mg omeprazole on a body surface area basis). Body weight and body weight gain were reduced and neurobehavioral or general developmental delays in the immediate post-weaning timeframe were evident at doses equal to or greater than 69 mg/kg/day (about 17 times an oral human dose of 40 mg esomeprazole or 40 mg omeprazole on a body surface area basis). In addition, decreased femur length, width and thickness of cortical bone, decreased thickness of the tibial growth plate and minimal to mild bone marrow hypocellularity were noted at doses equal to or greater than 14 mg/kg/day (about 3.4 times an oral human dose of 40 mg esomeprazole or 40 mg omeprazole on a body surface area basis). Physeal dysplasia in the femur was observed in offspring of rats treated with oral doses of esomeprazole magnesium at doses equal to or greater than 138 mg/kg/day (about 34 times an oral human dose of 40 mg esomeprazole or 40 mg omeprazole on a body surface area basis).

Effects on maternal bone were observed in pregnant and lactating rats in the pre- and postnatal toxicity study when esomeprazole magnesium was administered at oral doses of 14 to 280 mg/kg/day (about 3.4 to 68 times an oral human dose of 40 mg esomeprazole or 40 mg omeprazole on a body surface area basis). When rats were dosed from gestational day 7 through weaning on postnatal day 21, a statistically significant decrease in maternal femur weight of up to 14% (as compared to placebo treatment) was observed at doses equal to or greater than 138 mg/kg/day (about 34 times an oral human dose of 40 mg esomeprazole or 40 mg omeprazole on a body surface area basis).

A pre- and postnatal development study in rats with esomeprazole strontium (using equimolar doses compared to esomeprazole magnesium study) produced similar results in dams and pups as described above.

A follow up developmental toxicity study in rats with further time points to evaluate pup bone development from postnatal day 2 to adulthood was performed with esomeprazole magnesium at oral doses of 280 mg/kg/day (about 68 times an oral human dose of 40 mg on a body surface area basis) where esomeprazole administration was from either gestational day 7 or gestational day 16 until parturition. When maternal administration was confined to gestation only, there were no effects on bone physeal morphology in the offspring at any age.

8.2 Lactation

Risk Summary

Limited data suggest omeprazole may be present in human milk. There are no clinical data on the effects of omeprazole on the breastfed infant or on milk production. The developmental and health benefits of breastfeeding should be considered along with the mother's clinical need for PRILOSEC and any potential adverse effects on the breastfed infant from PRILOSEC or from the underlying maternal condition.

8.4 Pediatric Use

The safety and effectiveness of PRILOSEC have been established in pediatric patients 1 to 16 years for the treatment of symptomatic GERD, treatment of EE due to acid-mediated GERD, and maintenance of healing of EE due to acid-mediated GERD. Use of PRILOSEC in this age group is supported by adequate and well-controlled studies in adults and uncontrolled safety, efficacy, and pharmacokinetic studies performed in pediatric and adolescent patients [see Clinical Pharmacology (12.3), Clinical Studies (14.8)].

The safety and effectiveness of PRILOSEC have been established in pediatric patients 1 month to less than 1 year of age for the treatment of EE due to acid-mediated GERD and is supported by adequate and well-controlled studies in adults and safety, pharmacokinetic, and pharmacodynamic studies performed in pediatric patients [see Clinical Pharmacology (12.3)].

In the pediatric population, adverse reactions of the respiratory system were frequently reported in the entire (1 month to 16 year) age group. Otitis media was frequently reported in the 1 month to <1 year age group, fever was frequently reported in the 1 to <2 year age group, and accidental injuries were frequently reported in the 2 to 16 year age group [see Adverse Reactions (6.1)].

The safety and effectiveness of PRILOSEC have not been established in:

- patients less than 1 year of age for:
  - Treatment of symptomatic GERD
  - Maintenance of healing of EE due to acid-mediated GERD
- pediatric patients for:
  - Treatment of active duodenal ulcer
  - H. pylori eradication to reduce the risk of duodenal ulcer recurrence
  - Treatment of active benign gastric ulcer
  - Pathological hypersecretory conditions
- patients less than 1 month of age for any indication.

Juvenile Animal Data

Esomeprazole, an enantiomer of omeprazole, was shown to decrease body weight, body weight gain, femur weight, femur length, and overall growth at oral doses about 34 to 68 times a daily human dose of 40 mg esomeprazole or 40 mg omeprazole based on body surface area in a juvenile rat toxicity study. The animal to human dose multiples are based on the assumption of equal systemic exposure to esomeprazole in humans following oral administration of either 40 mg esomeprazole or 40 mg omeprazole.

A 28-day toxicity study with a 14-day recovery phase was conducted in juvenile rats with esomeprazole magnesium at doses of 70 to 280 mg/kg/day (about 17 to 68 times a daily oral human dose of 40 mg esomeprazole or 40 mg omeprazole on a body surface area basis). An increase in the number of deaths at the high dose of 280 mg/kg/day was observed when juvenile rats were administered esomeprazole magnesium from postnatal day 7 through postnatal day 35. In addition, doses equal to or greater than 140 mg/kg/day (about 34 times a daily oral human dose of 40 mg esomeprazole or 40 mg omeprazole on a body surface area basis), produced treatment-related decreases in body weight (approximately 14%) and body weight gain, decreases in femur weight and femur length, and affected overall growth. Comparable findings described above have also been observed in this study with another esomeprazole salt, esomeprazole strontium, at equimolar doses of esomeprazole.

8.5 Geriatric Use

Omeprazole was administered to over 2000 elderly individuals (≥ 65 years of age) in clinical trials in the U.S. and Europe. There were no differences in safety and effectiveness between the elderly and younger subjects. Other reported clinical experience has not identified differences in response between the elderly and younger subjects, but greater sensitivity of some older individuals cannot be ruled out.

Pharmacokinetic studies have shown the elimination rate was somewhat decreased in the elderly and bioavailability was increased. The plasma clearance of omeprazole was 250 mL/min (about half that of young volunteers) and its plasma half-life averaged one hour, about twice that of young healthy volunteers. However, no dosage adjustment is necessary in the elderly [see Clinical Pharmacology (12.3)].

8.6 Hepatic Impairment

In patients with hepatic impairment (Child-Pugh Class A, B, or C) exposure to omeprazole substantially increased compared to healthy subjects. Dosage reduction of PRILOSEC to 10 mg once daily is recommended for patients with hepatic impairment for maintenance of healing of EE [see Dosage and Administration (2.1), Clinical Pharmacology (12.3)].

8.7 Asian Population

In studies of healthy subjects, Asians had approximately a four-fold higher exposure than Caucasians. Dosage reduction of PRILOSEC to 10 mg once daily is recommended for Asian patients for maintenance of healing of EE [see Dosage and Administration (2.1), Clinical Pharmacology (12.5)].

10 OVERDOSAGE

Reports have been received of overdosage with omeprazole in humans. Doses ranged up to 2400 mg (120 times the usual recommended clinical dose). Manifestations were variable, but included confusion, drowsiness, blurred vision, tachycardia, nausea, vomiting, diaphoresis, flushing, headache, dry mouth, and other adverse reactions similar to those seen in normal clinical experience [see Adverse Reactions (6)]. Symptoms were transient, and no serious clinical outcome has been reported when PRILOSEC was taken alone. No specific antidote for omeprazole overdosage is known. Omeprazole is extensively protein bound and is, therefore, not readily dialyzable. In the event of overdosage, treatment should be symptomatic and supportive.

If over-exposure occurs, call your Poison Control Center at 1-800-222-1222 for current information on the management of poisoning or overdosage.

11 DESCRIPTION

The active ingredient in PRILOSEC (omeprazole magnesium) for delayed-release oral suspension, is 5-Methoxy-2-[[(4-methoxy-3,5-dimethyl-2-pyridinyl)methyl]sulfinyl]-1H-benzimidazole, magnesium salt (2:1).

Omeprazole magnesium is a white to off white powder with a melting point with degradation at 200°C. The salt is slightly soluble (0.25 mg/mL) in water at 25°C, and it is soluble in methanol. The half-life is highly pH dependent.

The empirical formula for omeprazole magnesium is (C17H18N3O3S)2 Mg, the molecular weight is 713.12 and the structural formula is:

Each packet of PRILOSEC for delayed-release oral suspension contains either 2.5 mg or 10 mg of omeprazole (equivalent to 2.8 mg or 11.2 mg of omeprazole magnesium trihydrate), in the form of enteric-coated granules with the following inactive ingredients: glyceryl monostearate, hydroxypropyl cellulose, hypromellose, magnesium stearate, methacrylic acid copolymer C, polysorbate, sugar spheres, talc, and triethyl citrate, and also inactive granules. The inactive granules are composed of the following ingredients: citric acid, crospovidone, dextrose, hydroxypropyl cellulose, iron oxide and xanthan gum. The omeprazole granules and inactive granules are constituted with water to form a suspension and are given by oral, nasogastric, or direct gastric administration.

12 CLINICAL PHARMACOLOGY

12.1 Mechanism of Action

Omeprazole belongs to a class of antisecretory compounds, the substituted benzimidazoles, that suppress gastric acid secretion by specific inhibition of the H^+/K^+ ATPase enzyme system at the secretory surface of the gastric parietal cell. Because this enzyme system is regarded as the acid (proton) pump within the gastric mucosa, omeprazole has been characterized as a gastric acid-pump inhibitor, in that it blocks the final step of acid production. This effect is dose-related and leads to inhibition of both basal and stimulated acid secretion irrespective of the stimulus.

12.2 Pharmacodynamics

Antisecretory Activity

After oral administration, the onset of the antisecretory effect of omeprazole occurs within one hour, with the maximum effect occurring within two hours. Inhibition of secretion is about 50% of maximum at 24 hours and the duration of inhibition lasts up to 72 hours. The antisecretory effect thus lasts far longer than would be expected from the very short (less than one hour) plasma half-life, apparently due to prolonged binding to the parietal H^+/K^+ ATPase enzyme. When the drug is discontinued, secretory activity returns gradually, over 3 to 5 days. The inhibitory effect of omeprazole on acid secretion increases with repeated once-daily dosing, reaching a plateau after four days.

Results from numerous studies of the antisecretory effect of multiple doses of 20 mg and 40 mg of omeprazole in healthy subjects and patients are shown below. The “max” value represents determinations at a time of maximum effect (2 to 6 hours after dosing), while “min” values are those 24 hours after the last dose of omeprazole.

Table 5: Range of Mean Values from Multiple Studies of the Mean Antisecretory Effects of Omeprazole After Multiple Daily Dosing
 | Omeprazole 20 mg |  | Omeprazole 40 mg
Parameter | Max | Min | Max | Min
% Decrease in Basal Acid Output | 78 [Single Studies] | 58-80 | 94 | 80-93
% Decrease in Peak Acid Output | 79 | 50-59 | 88 | 62-68
% Decrease in 24-hr. Intragastric Acidity |  | 80-97 |  | 92-94

Single daily oral doses of omeprazole ranging from a dose of 10 mg to 40 mg have produced 100% inhibition of 24-hour intragastric acidity in some patients.

Serum Gastrin Effects

In studies involving more than 200 patients, serum gastrin levels increased during the first 1 to 2 weeks of once-daily administration of therapeutic doses of omeprazole in parallel with inhibition of acid secretion. No further increase in serum gastrin occurred with continued treatment. In comparison with histamine H2-receptor antagonists, the median increases produced by 20 mg doses of omeprazole were higher (1.3 to 3.6 fold vs. 1.1 to 1.8 fold increase). Gastrin values returned to pretreatment levels, usually within 1 to 2 weeks after discontinuation of therapy.

Increased gastrin causes enterochromaffin-like cell hyperplasia and increased serum Chromogranin A (CgA) levels. The increased CgA levels may cause false positive results in diagnostic investigations for neuroendocrine tumors [see Warnings and Precautions (5.10)].

Enterochromaffin-like (ECL) Cell Effects

Human gastric biopsy specimens have been obtained from more than 3000 patients (both children and adults) treated with omeprazole in long-term clinical trials. The incidence of ECL cell hyperplasia in these studies increased with time; however, no case of ECL cell carcinoids, dysplasia, or neoplasia has been found in these patients. However, these studies are of insufficient duration and size to rule out the possible influence of long-term administration of omeprazole on the development of any premalignant or malignant conditions.

Other Effects

Systemic effects of omeprazole in the CNS, cardiovascular and respiratory systems have not been found to date. Omeprazole, given in oral doses of 30 or 40 mg for 2 to 4 weeks, had no effect on thyroid function, carbohydrate metabolism, or circulating levels of parathyroid hormone, cortisol, estradiol, testosterone, prolactin, cholecystokinin or secretin.

No effect on gastric emptying of the solid and liquid components of a test meal was demonstrated after a single dose of omeprazole 90 mg. In healthy subjects, a single intravenous dose of omeprazole (0.35 mg/kg) had no effect on intrinsic factor secretion. No systematic dose-dependent effect has been observed on basal or stimulated pepsin output in humans.

However, when intragastric pH is maintained at 4.0 or above, basal pepsin output is low, and pepsin activity is decreased.

As do other agents that elevate intragastric pH, omeprazole administered for 14 days in healthy subjects produced a significant increase in the intragastric concentrations of viable bacteria. The pattern of the bacterial species was unchanged from that commonly found in saliva. All changes resolved within three days of stopping treatment.

The course of Barrett’s esophagus in 106 patients was evaluated in a U.S. double-blind controlled study of PRILOSEC 40 mg twice daily for 12 months followed by 20 mg twice daily for 12 months or ranitidine 300 mg twice daily for 24 months. No clinically significant impact on Barrett’s mucosa by antisecretory therapy was observed. Although neosquamous epithelium developed during antisecretory therapy, complete elimination of Barrett’s mucosa was not achieved. No significant difference was observed between treatment groups in development of dysplasia in Barrett’s mucosa and no patient developed esophageal carcinoma during treatment. No significant differences between treatment groups were observed in development of ECL cell hyperplasia, corpus atrophic gastritis, corpus intestinal metaplasia, or colon polyps exceeding 3 mm in diameter.

12.3 Pharmacokinetics

Absorption

PRILOSEC for delayed-release oral suspension contains omeprazole magnesium granules and inactive granules to be administered in water. Absorption of omeprazole begins only after the gastro-resistant granules leave the stomach. The pharmacokinetics of omeprazole are time dependent, with higher plasma concentrations at steady state compared to after a single dose. The systemic exposure (AUC and Cmax) to omeprazole following once daily dosing of 20 mg delayed-release oral suspension for 5 days is 51% and 58% higher, respectively, than after the first dose. Peak plasma concentrations of omeprazole after repeated doses of delayed-release oral suspension occur within 1.5 to 2 hours. In healthy subjects, the plasma half-life is 0.5 to 1 hour.

Distribution

Protein binding is approximately 95%.

Elimination

Metabolism

Omeprazole is extensively metabolized by the cytochrome P450 (CYP) enzyme system. The major part of its metabolism is dependent on the polymorphically expressed CYP2C19, responsible for the formation of hydroxyomeprazole, the major metabolite in plasma. The remaining part is dependent on another specific isoform, CYP3A4, responsible for the formation of omeprazole sulphone.

Excretion

Following single dose oral administration of a buffered solution of omeprazole, little if any unchanged drug was excreted in urine. The majority of the dose (about 77%) was eliminated in urine as at least six metabolites. Two were identified as hydroxyomeprazole and the corresponding carboxylic acid. The remainder of the dose was recoverable in feces. This implies a significant biliary excretion of the metabolites of omeprazole. Three metabolites have been identified in plasma the sulfide and sulfone derivatives of omeprazole, and hydroxyomeprazole. These metabolites have very little or no antisecretory activity.

Combination Therapy with Antimicrobials

Omeprazole 40 mg daily was given in combination with clarithromycin 500 mg every 8 hours to healthy adult male subjects. The steady state plasma concentrations of omeprazole were increased (Cmax, AUC0-24, and T1/2 increases of 30%, 89% and 34% respectively) by the concomitant administration of clarithromycin. The observed increases in omeprazole plasma concentration were associated with the following pharmacological effects. The mean 24-hour gastric pH value was 5.2 when omeprazole was administered alone and 5.7 when co-administered with clarithromycin.

The plasma concentrations of clarithromycin and 14-hydroxy-clarithromycin were increased by the concomitant administration of omeprazole. For clarithromycin, the mean Cmax was 10% greater, the mean Cmin was 27% greater, and the mean AUC0-8 was 15% greater when clarithromycin was administered with omeprazole than when clarithromycin was administered alone. Similar results were seen for 14-hydroxy-clarithromycin, the mean Cmax was 45% greater, the mean Cmin was 57% greater, and the mean AUC0-8 was 45% greater. Clarithromycin concentrations in the gastric tissue and mucus were also increased by concomitant administration of omeprazole.

Table 6: Clarithromycin Tissue Concentrations 2 hours after Dose [Mean ± SD (μg/g)]
Tissue | Clarithromycin | Clarithromycin + Omeprazole
Antrum | 10.48 ± 2.01 (n = 5) | 19.96 ± 4.71 (n = 5)
Fundus | 20.81 ± 7.64 (n = 5) | 24.25 ± 6.37 (n = 5)
Mucus | 4.15 ± 7.74 (n = 4) | 39.29 ± 32.79 (n = 4)

Specific Populations

Geriatric Patients

The elimination rate of omeprazole was somewhat decreased in the elderly, and bioavailability was increased. Omeprazole was 76% bioavailable when a single 40 mg oral dose of omeprazole (buffered solution) was administered to healthy elderly volunteers, versus 58% in young volunteers given the same dose. Nearly 70% of the dose was recovered in urine as metabolites of omeprazole and no unchanged drug was detected. The plasma clearance of omeprazole was 250 mL/min (about half that of young volunteers) and its plasma half-life averaged one hour, about twice that of young healthy volunteers.

Pediatric Patients

2 to 16 Years of Age

The pharmacokinetics of omeprazole have been investigated in pediatric patients 2 to 16 years of age:

Table 7: Pharmacokinetic Parameters of Omeprazole Following Single and Repeated Oral Administration in Pediatric Populations Compared with Adults
Single or Repeated Oral Dosing/Parameter | Children [Data from single and repeated dose studies. Doses of 10, 20, and 40 mg omeprazole administered as suspension prepared from omeprazole magnesium delayed-release capsules.] ≤ 20 kg; 2-5 years; 10 mg | Children > 20 kg; 6-16 years; 20 mg | Adults [Data from a single and repeated dose study. Doses of 10, 20, and 40 mg omeprazole administered as delayed-release capsules.] (mean 76 kg); 23-29 years (n=12)
Single Dosing
Cmax [Plasma concentration adjusted to an oral dose of 1 mg/kg.] (ng/mL) | 288 (n=10) | 495 (n=49) | 668
AUC (ng h/mL) | 511 (n=7) | 1140 (n=32) | 1220
Repeated Dosing
Cmax (ng/mL) | 539 (n=4) | 851 (n=32) | 1458
AUC (ng h/mL) | 1179 (n=2) | 2276 (n=23) | 3352

Following comparable mg/kg doses of omeprazole, younger children (2 to 5 years of age) have lower AUCs than children 6 to 16 years of age or adults; AUCs of the latter two groups did not differ [see Dosage and Administration (2)].

1 to 11 Months of Age

A population pharmacokinetics model was used to determine appropriate doses of PRILOSEC in pediatric patients 1 month to less than 1 year of age for treatment (up to 6 weeks) of erosive esophagitis due to acid-mediated GERD. The model was based on data from three studies in 64 children 0.5 month to 16 years of age. Only limited data were available in children younger than the age of 1 year. Omeprazole was administered to the pediatric patients in these studies as an oral suspension prepared from the delayed-release capsules. Pediatric doses were simulated in the age group of 1 to 11 months, to achieve comparable omeprazole exposures with adults following treatment with 20 mg once daily [see Dosage and Administration (2.2)].

Racial or Ethnic Groups

[See Clinical Pharmacology (12.5)].

Patients with Renal Impairment

In patients with chronic renal impairment (creatinine clearance between 10 and 62 mL/min/1.73 m^2), the disposition of omeprazole was very similar to that in healthy subjects, although there was a slight increase in bioavailability. Because urinary excretion is a primary route of excretion of omeprazole metabolites, their elimination slowed in proportion to the decreased creatinine clearance. This increase in bioavailability is not considered to be clinically meaningful.

Patients with Hepatic Impairment

In patients with chronic hepatic disease classified as Child-Pugh Class A (n=3), B (n=4) and C (n=1), the bioavailability increased to approximately 100% compared to healthy subjects, reflecting decreased first-pass effect, and the plasma half-life of the drug increased to nearly 3 hours compared with the half-life in healthy subjects of 0.5 to 1 hour. Plasma clearance averaged 70 mL/min, compared with a value of 500 to 600 mL/min in healthy subjects [see Dosage and Administration (2.1), Use in Specific Populations (8.6)].

Drug Interaction Studies

Effect of Omeprazole on Other Drugs

Omeprazole is a time-dependent inhibitor of CYP2C19 and can increase the systemic exposure of co-administered drugs that are CYP2C19 substrates. In addition, administration of omeprazole increases intragastric pH and can alter the systemic exposure of certain drugs that exhibit pH-dependent solubility.

Antiretrovirals

For some antiretroviral drugs, such as rilpivirine, atazanavir and nelfinavir, decreased serum concentrations have been reported when given together with omeprazole [see Drug Interactions (7)].

Rilpivirine: Following multiple doses of rilpivirine (150 mg, daily) and omeprazole (20 mg, daily), AUC was decreased by 40%, Cmax by 40%, and Cmin by 33% for rilpivirine.

Nelfinavir: Following multiple doses of nelfinavir (1250 mg, twice daily) and omeprazole (40 mg daily), AUC was decreased by 36% and 92%, Cmax by 37% and 89% and Cmin by 39% and 75% respectively for nelfinavir and M8.

Atazanavir: Following multiple doses of atazanavir (400 mg, daily) and omeprazole (40 mg, daily, 2 hours before atazanavir), AUC was decreased by 94%, Cmax by 96%, and Cmin by 95%.

Saquinavir: Following multiple dosing of saquinavir/ritonavir (1000/100 mg) twice daily for 15 days with omeprazole 40 mg daily co-administered days 11 to 15.

AUC was increased by 82%, Cmax by 75%, and Cmin by 106%. The mechanism behind this interaction is not fully elucidated.

Clopidogrel

In a crossover clinical study, 72 healthy subjects were administered clopidogrel (300 mg loading dose followed by 75 mg per day) alone and with omeprazole (80 mg at the same time as clopidogrel) for 5 days. The exposure to the active metabolite of clopidogrel was decreased by 46% (Day 1) and 42% (Day 5) when clopidogrel and omeprazole were administered together.

Results from another crossover study in healthy subjects showed a similar pharmacokinetic interaction between clopidogrel (300 mg loading dose/75 mg daily maintenance dose) and omeprazole 80 mg daily when co-administered for 30 days. Exposure to the active metabolite of clopidogrel was reduced by 41% to 46% over this time period.

In another study, 72 healthy subjects were given the same doses of clopidogrel and 80 mg omeprazole but the drugs were administered 12 hours apart; the results were similar, indicating that administering clopidogrel and omeprazole at different times does not prevent their interaction [see Warnings and Precautions (5.6), Drug Interactions (7)].

Mycophenolate Mofetil

Administration of omeprazole 20 mg twice daily for 4 days and a single 1000 mg dose of MMF approximately one hour after the last dose of omeprazole to 12 healthy subjects in a cross-over study resulted in a 52% reduction in the Cmax and 23% reduction in the AUC of MPA [see Drug Interactions (7)].

Cilostazol

Omeprazole acts as an inhibitor of CYP2C19. Omeprazole, given in doses of 40 mg daily for one week to 20 healthy subjects in cross-over study, increased Cmax and AUC of cilostazol by 18% and 26% respectively. The Cmax and AUC of one of the active metabolites, 3,4- dihydro-cilostazol, which has 4-7 times the activity of cilostazol, were increased by 29% and 69%, respectively. Co-administration of cilostazol with omeprazole is expected to increase concentrations of cilostazol and the above mentioned active metabolite [see Drug Interactions (7)].

Diazepam

Concomitant administration of omeprazole 20 mg once daily and diazepam 0.1 mg/kg given intravenously resulted in 27% decrease in clearance and 36% increase in diazepam half-life [see Drug Interactions (7)].

Digoxin

Concomitant administration of omeprazole 20 mg once daily and digoxin in healthy subjects increased the bioavailability of digoxin by 10% (30% in two subjects) [see Drug Interactions (7)].

Effect of Other Drugs on Omeprazole

Voriconazole

Concomitant administration of omeprazole and voriconazole (a combined inhibitor of CYP2C19 and CYP3A4) resulted in more than doubling of the omeprazole exposure. When voriconazole (400 mg every 12 hours for one day, followed by 200 mg once daily for 6 days) was given with omeprazole (40 mg once daily for 7 days) to healthy subjects, the steady-state Cmax and AUC0-24 of omeprazole significantly increased: an average of 2 times (90% CI: 1.8, 2.6) and 4 times (90% CI: 3.3, 4.4), respectively, as compared to when omeprazole was given without voriconazole [see Drug Interactions (7)].

12.4 Microbiology

Omeprazole and clarithromycin dual therapy and omeprazole, clarithromycin and amoxicillin triple therapy have been shown to be active against most strains of Helicobacter pylori in vitro and in clinical infections [see Indications and Usage (1.2), Clinical Studies (14.2)].

Helicobacter pylori

Susceptibility testing of H. pylori isolates was performed for amoxicillin and clarithromycin using agar dilution methodology^1, and minimum inhibitory concentrations (MICs) were determined.

Standardized susceptibility test procedures require the use of laboratory control microorganisms to control the technical aspects of the laboratory procedures.

Pretreatment Resistance

Clarithromycin pretreatment resistance rates were 3.5% (4/113) in the omeprazole/clarithromycin dual therapy studies (4 and 5) and 9.3% (41/439) in omeprazole/clarithromycin/amoxicillin triple therapy studies (1, 2 and 3).

Amoxicillin pretreatment susceptible isolates (≤ 0.25 µg/mL) were found in 99.3% (436/439) of the patients in the omeprazole/clarithromycin/amoxicillin triple therapy studies (1, 2, and 3). Amoxicillin pretreatment minimum inhibitory concentrations (MICs) > 0.25 µg/mL occurred in 0.7% (3/439) of the patients, all of whom were in the clarithromycin and amoxicillin study arm. One patient had an unconfirmed pretreatment amoxicillin minimum inhibitory concentration (MIC) of > 256 µg/mL by Etest®.

Table 8: Clarithromycin Susceptibility Test Results and Clinical/Bacteriological Outcomes
Clarithromycin Susceptibility Test Results and Clinical/Bacteriological Outcomes [Includes only patients with pretreatment clarithromycin susceptibility test results.]
Clarithromycin Pretreatment Results |  | Clarithromycin Post-treatment Results
 |  | H. pylori negative – eradicated | H. pylori positive – not eradicated; Post-treatment susceptibility results
 |  |  | S [Susceptible (S) MIC ≤ 0.25 μg/mL, Intermediate (I) MIC 0.5-1.0 μg/mL, Resistant (R) MIC ≥ 2 μg/mL.] | I | R | No MIC
Dual Therapy – (omeprazole 40 mg once daily/clarithromycin 500 three times daily for 14 days followed by omeprazole 20 mg once daily for another 14 days) (Studies 4, 5)
Susceptible | 108 | 72 | 1 |  | 26 | 9
Intermediate | 1 |  |  |  | 1
Resistant | 4 |  |  |  | 4
Triple Therapy – (omeprazole 20 mg twice daily/clarithromycin 500 mg twice daily/amoxicillin 1 g twice daily for 10 days – Studies 1, 2, 3; followed by omeprazole 20 mg once daily for another 18 days – Studies 1, 2)
Susceptible | 171 | 153 | 7 |  | 3 | 8
Intermediate
Resistant | 14 | 4 | 1 |  | 6 | 3

Patients not eradicated of H. pylori following omeprazole/clarithromycin/amoxicillin triple therapy or omeprazole/clarithromycin dual therapy will likely have clarithromycin resistant H. pylori isolates. Therefore, clarithromycin susceptibility testing should be done, if possible. Patients with clarithromycin resistant H. pylori should not be treated with any of the following: omeprazole/clarithromycin dual therapy, omeprazole/clarithromycin/amoxicillin triple therapy, or other regimens which include clarithromycin as the sole antimicrobial agent.

Amoxicillin Susceptibility Test Results and Clinical/Bacteriological Outcomes

In the triple therapy clinical trials, 84.9% (157/185) of the patients in the omeprazole/clarithromycin/amoxicillin treatment group who had pretreatment amoxicillin susceptible MICs (≤ 0.25 µg/mL) were eradicated of H. pylori and 15.1% (28/185) failed therapy. Of the 28 patients who failed triple therapy, 11 had no post-treatment susceptibility test results and 17 had post-treatment H. pylori isolates with amoxicillin susceptible MICs. Eleven of the patients who failed triple therapy also had post-treatment H. pylori isolates with clarithromycin resistant MICs.

Susceptibility Test for Helicobacter pylori

For susceptibility testing information about Helicobacter pylori, see Microbiology section in prescribing information for clarithromycin and amoxicillin.

Effects on Gastrointestinal Microbial Ecology

Decreased gastric acidity due to any means including proton pump inhibitors, increases gastric counts of bacteria normally present in the gastrointestinal tract. Treatment with proton pump inhibitors may lead to slightly increased risk of gastrointestinal infections such as Salmonella and Campylobacter and, in hospitalized patients, possibly also Clostridium difficile.

12.5 Pharmacogenomics

CYP2C19, a polymorphic enzyme, is involved in the metabolism of omeprazole. The CYP2C19*1 allele is fully functional while the CYP2C19*2 and *3 alleles are nonfunctional. There are other alleles associated with no or reduced enzymatic function. Patients carrying two fully functional alleles are extensive metabolizers and those carrying two loss-of-function alleles are poor metabolizers. In extensive metabolizers, omeprazole is primarily metabolized by CYP2C19. The systemic exposure to omeprazole varies with a patient’s metabolism status: poor metabolizers > intermediate metabolizers > extensive metabolizers. Approximately 3% of Caucasians and 15 to 20% of Asians are CYP2C19 poor metabolizers.

In a pharmacokinetic study of single 20 mg omeprazole dose, the AUC of omeprazole in Asian subjects was approximately four-fold of that in Caucasians [see Dosage and Administration (2.1), Use in Specific Populations (8.7)].

13 NONCLINICAL TOXICOLOGY

13.1 Carcinogenesis, Mutagenesis, Impairment of Fertility

In two 24-month carcinogenicity studies in rats, omeprazole at daily doses of 1.7, 3.4, 13.8, 44.0 and 140.8 mg/kg/day (about 0.4 to 34 times a human dose of 40 mg/day, as expressed on a body surface area basis) produced gastric ECL cell carcinoids in a dose-related manner in both male and female rats; the incidence of this effect was markedly higher in female rats, which had higher blood levels of omeprazole. Gastric carcinoids seldom occur in the untreated rat. In addition, ECL cell hyperplasia was present in all treated groups of both sexes. In one of these studies, female rats were treated with 13.8 mg omeprazole/kg/day (about 3.4 times a human dose of 40 mg/day, based on body surface area) for one year, and then followed for an additional year without the drug. No carcinoids were seen in these rats. An increased incidence of treatment-related ECL cell hyperplasia was observed at the end of one year (94% treated vs. 10% controls). By the second year the difference between treated and control rats was much smaller (46% vs. 26%) but still showed more hyperplasia in the treated group. Gastric adenocarcinoma was seen in one rat (2%). No similar tumor was seen in male or female rats treated for two years. For this strain of rat no similar tumor has been noted historically, but a finding involving only one tumor is difficult to interpret. In a 52-week toxicity study in Sprague-Dawley rats, brain astrocytomas were found in a small number of males that received omeprazole at dose levels of 0.4, 2, and 16 mg/kg/day (about 0.1 to 3.9 times the human dose of 40 mg/day, based on a body surface area basis). No astrocytomas were observed in female rats in this study. In a 2-year carcinogenicity study in Sprague-Dawley rats, no astrocytomas were found in males or females at the high dose of 140.8 mg/kg/day (about 34 times the human dose of 40 mg/day on a body surface area basis). A 78-week mouse carcinogenicity study of omeprazole did not show increased tumor occurrence, but the study was not conclusive. A 26-week p53 (+/-) transgenic mouse carcinogenicity study was not positive.

Omeprazole was positive for clastogenic effects in an in vitro human lymphocyte chromosomal aberration assay, in one of two in vivo mouse micronucleus tests, and in an in vivo bone marrow cell chromosomal aberration assay. Omeprazole was negative in the in vitro Ames test, an in vitro mouse lymphoma cell forward mutation assay, and an in vivo rat liver DNA damage assay.

Omeprazole at oral doses up to 138 mg/kg/day in rats (about 34 times an oral human dose of 40 mg on a body surface area basis) was found to have no effect on fertility and reproductive performance.

In 24-month carcinogenicity studies in rats, a dose-related significant increase in gastric carcinoid tumors and ECL cell hyperplasia was observed in both male and female animals [see Warnings and Precautions (5)]. Carcinoid tumors have also been observed in rats subjected to fundectomy or long-term treatment with other proton pump inhibitors or high doses of H2-receptor antagonists.

14 CLINICAL STUDIES

14.1 Active Duodenal Ulcer

In a multicenter, double-blind, placebo-controlled study of 147 patients with endoscopically documented duodenal ulcer, the percentage of patients healed (per protocol) at 2 and 4 weeks was significantly higher with omeprazole magnesium delayed-release capsules 20 mg once daily than with placebo (p ≤ 0.01).

Treatment of Active Duodenal Ulcer % of Patients Healed
 | omeprazole magnesium delayed-release capsules; 20 mg a.m.; (n=99) | Placebo; a.m.; (n=48)
Week 2 | 41 [(p≤0.01)] | 13
Week 4 | 75 | 27

Complete daytime and nighttime pain relief occurred significantly faster (p ≤ 0.01) in patients treated with omeprazole magnesium delayed-release capsules 20 mg than in patients treated with placebo. At the end of the study, significantly more patients who had received omeprazole magnesium delayed-release capsules had complete relief of daytime pain (p ≤ 0.05) and nighttime pain (p ≤ 0.01).

In a multicenter, double-blind study of 293 patients with endoscopically documented duodenal ulcer, the percentage of patients healed (per protocol) at 4 weeks was significantly higher with omeprazole magnesium delayed-release capsules 20 mg once daily than with ranitidine 150 mg b.i.d. (p < 0.01).

Treatment of Active Duodenal Ulcer % of Patients Healed
 | omeprazole magnesium delayed-release capsules; 20 mg a.m.; (n = 145) | Ranitidine; 150 mg twice daily; (n = 148)
Week 2 | 42 | 34
Week 4 | 82 [(p < 0.01)] | 63

Healing occurred significantly faster in patients treated with omeprazole magnesium delayed-release capsules than in those treated with ranitidine 150 mg b.i.d. (p < 0.01).

In a foreign multinational, randomized, double-blind study of 105 patients with endoscopically documented duodenal ulcer, 20 mg and 40 mg of omeprazole magnesium delayed-release capsules were compared with 150 mg b.i.d. of ranitidine at 2, 4, and 8 weeks. At 2 and 4 weeks, both doses of PRILOSEC were statistically superior (per protocol) to ranitidine, but 40 mg was not superior to 20 mg of omeprazole magnesium delayed-release capsules, and at 8 weeks there was no significant difference between any of the active drugs.

Treatment of Active Duodenal Ulcer % of Patients Healed
 | omeprazole magnesium delayed-release capsules |  | Ranitidine
 | 20 mg; (n = 34) | 40 mg; (n = 36) | 150 mg twice daily; (n = 35)
Week 2 | 83 [(p ≤ 0.01)] | 83 | 53
Week 4 | 97 | 100 | 82
Week 8 | 100 | 100 | 94

14.2 H. pylori Eradication in Patients with Duodenal Ulcer Disease

Triple Therapy (omeprazole magnesium delayed-release capsules/clarithromycin/amoxicillin)

Three US, randomized, double-blind clinical studies in patients with H. pylori infection and duodenal ulcer disease (n = 558) compared omeprazole magnesium delayed-release capsules plus clarithromycin plus amoxicillin with clarithromycin plus amoxicillin. Two studies (1 and 2) were conducted in patients with an active duodenal ulcer, and the other study (3) was conducted in patients with a history of a duodenal ulcer in the past 5 years but without an ulcer present at the time of enrollment. The dose regimen in the studies was omeprazole magnesium delayed-release capsules 20 mg twice daily plus clarithromycin 500 mg twice daily plus amoxicillin 1 g twice daily for 10 days; or clarithromycin 500 mg twice daily plus amoxicillin 1 g twice daily for 10 days. In studies 1 and 2, patients who took the omeprazole regimen also received an additional 18 days of omeprazole magnesium delayed-release capsules 20 mg once daily. Endpoints studied were eradication of H. pylori and duodenal ulcer healing (studies 1 and 2 only). H. pylori status was determined by CLOtest®, histology and culture in all three studies. For a given patient, H. pylori was considered eradicated if at least two of these tests were negative, and none was positive.

The combination of omeprazole plus clarithromycin plus amoxicillin was effective in eradicating H. pylori.

Table 9: Per- Protocol and Intent-to-Treat H. pylori Eradication Rates % of Patients Cured [95% Confidence Interval]
 | Omeprazole magnesium delayed-release capsules +clarithromycin +amoxicillin |  | Clarithromycin +amoxicillin
 | Per-Protocol [Patients were included in the analysis if they had confirmed duodenal ulcer disease (active ulcer, studies 1 and 2; history of ulcer within 5 years, study 3) and H. pylori infection at baseline defined as at least two of three positive endoscopic tests from CLOtest®, histology, and/or culture. Patients were included in the analysis if they completed the study. Additionally, if patients dropped out of the study due to an adverse event related to the study drug, they were included in the analysis as failures of therapy. The impact of eradication on ulcer recurrence has not been assessed in patients with a past history of ulcer.] | Intent-to-Treat [Patients were included in the analysis if they had documented H. pylori infection at baseline and had confirmed duodenal ulcer disease. All dropouts were included as failures of therapy.] | Per-Protocol | Intent-to-Treat
Study 1 | 77 [(p < 0.05) versus clarithromycin plus amoxicillin.] [64, 86]; (n = 64) | 69 [57, 79]; (n = 80) | 43 [31, 56]; (n = 67) | 37 [27, 48]; (n = 84)
Study 2 | 78 [67, 88]; (n = 65) | 73 [61, 82]; (n = 77) | 41 [29, 54]; (n = 68) | 36 [26, 47]; (n = 83)
Study 3 | 90 [80, 96]; (n = 69) | 83 [74, 91]; (n = 84) | 33 [24, 44]; (n = 93) | 32 [23, 42]; (n = 99)

Dual Therapy (omeprazole magnesium delayed-release capsules/clarithromycin)

Four randomized, double-blind, multi-center studies (4, 5, 6, and 7) evaluated omeprazole magnesium delayed-release capsules 40 mg once daily plus clarithromycin 500 mg three times daily for 14 days, followed by omeprazole magnesium delayed-release capsules 20 mg once daily, (Studies 4, 5, and 7) or by omeprazole magnesium delayed-release capsules 40 mg once daily (Study 6) for an additional 14 days in patients with active duodenal ulcer associated with H. pylori. Studies 4 and 5 were conducted in the U.S. and Canada and enrolled 242 and 256 patients, respectively. H. pylori infection and duodenal ulcer were confirmed in 219 patients in Study 4 and 228 patients in Study 5. These studies compared the combination regimen to omeprazole magnesium delayed-release capsules and clarithromycin monotherapies. Studies 6 and 7 were conducted in Europe and enrolled 154 and 215 patients, respectively. H. pylori infection and duodenal ulcer were confirmed in 148 patients in Study 6 and 208 patients in Study 7. These studies compared the combination regimen with omeprazole monotherapy. The results for the efficacy analyses for these studies are described below. H. pylori eradication was defined as no positive test (culture or histology) at 4 weeks following the end of treatment, and two negative tests were required to be considered eradicated of H. pylori. In the per-protocol analysis, the following patients were excluded: dropouts, patients with missing H. pylori tests post-treatment, and patients that were not assessed for H. pylori eradication because they were found to have an ulcer at the end of treatment.

The combination of omeprazole and clarithromycin was effective in eradicating H. pylori.

Table 10: H. pylori Eradication Rates (Per-Protocol Analysis at 4 to 6 Weeks) % of Patients Cured [95% Confidence Interval]
 | Omeprazole magnesium delayed-release capsules + Clarithromycin | Omeprazole magnesium delayed-release capsules | Clarithromycin
US Studies
Study 4 | 74 [60, 85] [Statistically significantly higher than clarithromycin monotherapy (p < 0.05).] , [Statistically significantly higher than omeprazole monotherapy (p < 0.05).]; (n = 53) | 0 [0, 7]; (n = 54) | 31 [18, 47]; (n = 42)
Study 5 | 64 [51, 76],; (n = 61) | 0 [0, 6]; (n = 59) | 39 [24, 55]; (n = 44)
Non US Studies
Study 6 | 83 [71, 92]; (n = 60) | 1 [0, 7]; (n = 74) | N/A
Study 7 | 74 [64, 83]; (n = 86) | 1 [0, 6]; (n = 90) | N/A

Ulcer healing was not significantly different when clarithromycin was added to omeprazole therapy compared with omeprazole therapy alone.

The combination of omeprazole and clarithromycin was effective in eradicating H. pylori and reduced duodenal ulcer recurrence.

Table 11: Duodenal Ulcer Recurrence Rates by H. pylori Eradication Status % of Patients with Ulcer Recurrence
 | H. pylori eradicated [H. pylori eradication status assessed at same time point as ulcer recurrence.] | H. pylori not eradicated
US Studies [Combined results for omeprazole magnesium delayed-release capsules + clarithromycin, omeprazole magnesium delayed-release capsules, and clarithromycin treatment arms.]
6 months post-treatment
Study 4 | 35 [(p ≤ 0.01) versus proportion with duodenal ulcer recurrence who were not H. pylori eradicated.]; (n=49) | 60; (n=88)
Study 5 | 8; (n=53) | 60; (n=106)
Non US Studies [Combined results for omeprazole magnesium delayed-release capsules + clarithromycin and omeprazole magnesium delayed-release capsules treatment arms.]
6 months post-treatment
Study 6 | 5; (n=43) | 46; (n=78)
Study 7 | 6; (n=53) | 43; (n=107)
12 months post-treatment
Study 6 | 5; (n=39) | 68; (n=71)

14.3 Active Benign Gastric Ulcer

In a U.S. multicenter, double-blind study of omeprazole 40 mg once daily, 20 mg once daily, and placebo in 520 patients with endoscopically diagnosed gastric ulcer, the following results were obtained.

Treatment of Gastric Ulcer % of Patients Healed (All Patients Treated)
 | omeprazole magnesium delayed-release capsules; 20 mg once daily; (n = 202) | omeprazole magnesium delayed-release capsules; 40 mg once daily; (n = 214) | Placebo; (n = 104)
Week 4 | 47.5 [(p < 0.01) omeprazole magnesium delayed-release capsules 40 mg or 20 mg versus placebo.] | 55.6 | 30.8
Week 8 | 74.8 | 82.7, [(p < 0.05) omeprazole magnesium delayed-release capsules 40 mg versus 20 mg.] | 48.1

For the stratified groups of patients with ulcer size less than or equal to 1 cm, no difference in healing rates between 40 mg and 20 mg was detected at either 4 or 8 weeks. For patients with ulcer size greater than 1 cm, 40 mg was significantly more effective than 20 mg at 8 weeks.

In a foreign, multinational, double-blind study of 602 patients with endoscopically diagnosed gastric ulcer, omeprazole 40 mg once daily, 20 mg once daily, and ranitidine 150 mg twice a day were evaluated.

Treatment of Gastric Ulcer % of Patients Healed (All Patients Treated)
 | omeprazole magnesium delayed-release capsules; 20 mg once daily; (n = 200) | omeprazole magnesium delayed-release capsules; 40 mg once daily; (n = 187) | Ranitidine; 150 mg twice daily; (n = 199)
Week 4 | 63.5 | 78.1 [(p < 0.01) omeprazole magnesium delayed-release capsules 40 mg versus ranitidine.] , [(p < 0.01) omeprazole magnesium delayed-release capsules 40 mg versus 20 mg.] | 56.3
Week 8 | 81.5 | 91.4, | 78.4

14.4 Symptomatic GERD

A placebo-controlled study was conducted in Scandinavia to compare the efficacy of omeprazole 20 mg or 10 mg once daily for up to 4 weeks in the treatment of heartburn and other symptoms in GERD patients without EE. Results are shown below.

% Successful Symptomatic Outcome [Defined as complete resolution of heartburn.]
 | omeprazole magnesium delayed-release capsules; 20 mg a.m. | omeprazole magnesium delayed-release capsules; 10 mg a.m. | Placebo; a.m.
All patients | 46 [(p < 0.005) versus 10 mg.] , [(p < 0.005) versus placebo.]; (n = 205) | 31; (n = 199) | 13; (n = 105)
Patients with confirmed GERD | 56,; (n = 115) | 36; (n = 109) | 14; (n = 59)

14.5 EE due to Acid-Mediated GERD

In a US multicenter, double-blind, placebo-controlled study of 20 mg or 40 mg of omeprazole magnesium delayed-release capsules in patients with symptoms of GERD and endoscopically diagnosed EE of grade 2 or above, the percentage healing rates (per protocol) were as follows:

 | 20 mg; omeprazole magnesium delayed-release capsules; (n = 83) | 40 mg; omeprazole magnesium delayed-release capsules; (n = 87) | Placebo; (n = 43)
Week 4 | 39 [(p < 0.01) omeprazole magnesium delayed-release capsules versus placebo.] | 45 | 7
Week 8 | 74 | 75 | 14

In this study, the 40 mg dose was not superior to the 20 mg dose of omeprazole magnesium delayed-release capsules in the percentage healing rate. Other controlled clinical trials have also shown that omeprazole magnesium delayed-release capsules is effective in severe GERD. In comparisons with histamine H2-receptor antagonists in patients with EE, grade 2 or above, omeprazole magnesium delayed-release capsules in a dose of 20 mg was significantly more effective than the active controls. Complete daytime and nighttime heartburn relief occurred significantly faster (p < 0.01) in patients treated with omeprazole magnesium delayed-release capsules than in those taking placebo or histamine H2-receptor antagonists.

In this and five other controlled GERD studies, significantly more patients taking 20 mg omeprazole (84%) reported complete relief of GERD symptoms than patients receiving placebo (12%).

14.6 Maintenance of Healing of EE due to Acid-Mediated GERD

In a U.S. double-blind, randomized, multicenter, placebo controlled study, two dose regimens of omeprazole magnesium delayed-release capsules were studied in patients with endoscopically confirmed healed esophagitis. Results to determine maintenance of healing of EE are shown below.

Life Table Analysis
 | omeprazole magnesium delayed-release capsules; 20 mg once daily; (n = 138) | omeprazole magnesium delayed-release capsules; 20 mg 3 days per week; (n = 137) | Placebo; (n = 131)
Percent in endoscopic remission at 6 months | 70 [(p < 0.01) omeprazole magnesium delayed-release capsules 20 mg once daily versus omeprazole magnesium delayed-release capsules 20 mg 3 consecutive days per week or placebo.] | 34 | 11

In an international multicenter double-blind study, omeprazole magnesium delayed-release capsules 20 mg daily and 10 mg daily were compared with ranitidine 150 mg twice daily in patients with endoscopically confirmed healed esophagitis. The table below provides the results of this study for maintenance of healing of EE.

Life Table Analysis
 | omeprazole magnesium delayed-release capsules; 20 mg once daily; (n = 131) | omeprazole magnesium delayed-release capsules; 10 mg once daily; (n = 133) | Ranitidine; 150 mg twice daily; (n = 128)
Percent in endoscopic remission at 12 months | 77 [(p = 0.01) omeprazole magnesium delayed-release capsules 20 mg once daily versus omeprazole magnesium delayed-release capsules 10 mg once daily or Ranitidine.] | 58 [(p = 0.03) omeprazole magnesium delayed-release capsules 10 mg once daily versus Ranitidine.] | 46

In patients who initially had grades 3 or 4 erosive esophagitis, for maintenance after healing 20 mg daily of omeprazole magnesium delayed-release capsules was effective, while 10 mg did not demonstrate effectiveness.

14.7 Pathological Hypersecretory Conditions

In open studies of 136 patients with pathological hypersecretory conditions, such as Zollinger-Ellison (ZE) syndrome with or without multiple endocrine adenomas, omeprazole magnesium delayed-release capsules significantly inhibited gastric acid secretion and controlled associated symptoms of diarrhea, anorexia, and pain. Doses ranging from 20 mg every other day to 360 mg per day maintained basal acid secretion below 10 mEq/hr in patients without prior gastric surgery, and below 5 mEq/hr in patients with prior gastric surgery.

Initial doses were titrated to the individual patient need, and adjustments were necessary with time in some patients [see Dosage and Administration (2)]. Omeprazole magnesium delayed-release capsules was well tolerated at these high dose levels for prolonged periods (> 5 years in some patients). In most ZE patients, serum gastrin levels were not modified by omeprazole magnesium delayed-release capsules. However, in some patients serum gastrin increased to levels greater than those present prior to initiation of omeprazole therapy. At least 11 patients with ZE syndrome on long-term treatment with omeprazole magnesium delayed-release capsules developed gastric carcinoids. These findings are believed to be a manifestation of the underlying condition, which is known to be associated with such tumors, rather than the result of the administration of omeprazole magnesium delayed-release capsules [see Adverse Reactions (6)].

14.8 Pediatric Studies for the Treatment of Symptomatic GERD, Treatment of EE due to Acid-Mediated GERD, and Maintenance of Healing of EE due to Acid-Mediated GERD

Treatment of Symptomatic GERD

The effectiveness of omeprazole magnesium delayed-release capsules for the treatment of symptomatic GERD in pediatric patients 1 to 16 years of age is based in part on data obtained from 125 pediatric patients in two uncontrolled clinical studies.

The first study enrolled 12 pediatric patients 1 to 2 years of age with a history of clinically diagnosed GERD. Patients were administered a single dose of omeprazole (0.5 mg/kg, 1 mg/kg, or 1.5 mg/kg) for 8 weeks as an open capsule in 8.4% sodium bicarbonate solution. Seventy-five percent (9/12) of the patients had vomiting/regurgitation episodes decreased from baseline by at least 50%.

The second study enrolled 113 pediatric patients 2 to 16 years of age with a history of symptoms suggestive of symptomatic GERD. Patients were administered a single dose of omeprazole (10 mg or 20 mg, based on body weight) for 4 weeks either as an intact capsule or as an open capsule in applesauce. Successful response was defined as no moderate or severe episodes of either pain-related symptoms or vomiting/regurgitation during the last 4 days of treatment. Results showed success rates of 60% (9/15; 10 mg omeprazole) and 59% (58/98; 20 mg omeprazole), respectively.

Treatment of EE due to Acid-Mediated GERD

In an uncontrolled, open-label dose-titration study, for the treatment of EE in pediatric patients 1 to 16 years of age, required doses that ranged from 0.7 to 3.5 mg/kg/day (80 mg/day). Doses were initiated at 0.7 mg/kg/day. Doses were increased in increments of 0.7 mg/kg/day (if intraesophageal pH showed a pH of < 4 for less than 6% of a 24-hour study). After titration, patients remained on treatment for 3 months. Forty-four percent of the patients were healed on a dose of 0.7 mg/kg body weight; most of the remaining patients were healed with 1.4 mg/kg after an additional 3 months’ treatment. EE was healed in 51 of 57 (90%) children who completed the first course of treatment in the healing phase of the study. In addition, after 3 months of treatment, 33% of the children had no overall symptoms, 57% had mild reflux symptoms, and 40% had less frequent regurgitation/vomiting.

Maintenance of Healing of EE due to Acid-Mediated GERD

In an uncontrolled, open-label study of maintenance of healing of EE in 46 pediatric patients 1 to 16 years of age, 54% of patients required half the healing dose. The remaining patients increased the healing dose (0.7 to a maximum of 2.8 mg/kg/day) either for the entire maintenance period, or returned to half the dose before completion. Of the 46 patients who entered the maintenance phase, 19 (41%) had no relapse during follow-up (range 4 to 25 months). In addition, maintenance therapy in EE patients resulted in 63% of patients having no overall symptoms.

15 REFERENCES

1. Clinical and Laboratory Standards Institute (CLSI). Methods for Dilution Antimicrobial Susceptibility Tests for Bacteria That Grow Aerobically; Approved Standard—Tenth Edition. CLSI Document M07-A10, Clinical and Laboratory Standards Institute, 950 West Valley Road, Suite 2500, Wayne, Pennsylvania, 19087, USA 2015.

16 HOW SUPPLIED/STORAGE AND HANDLING

PRILOSEC (omeprazole magnesium) for delayed-release oral suspension, 2.5 mg or 10 mg omeprazole, is supplied as a unit dose packet containing a fine yellow powder, consisting of white to brownish omeprazole magnesium granules and pale yellow inactive granules. PRILOSEC unit dose packets are supplied as follows:

NDC 70515-625-01 unit dose packages of 30: 2.5 mg packets

NDC 70515-610-01 unit dose packages of 30: 10 mg packets

Storage

Store PRILOSEC for delayed-release oral suspension at 25°C (77°F); excursions permitted to 15 – 30°C (59 – 86°F). [See USP Controlled Room Temperature.]

17 PATIENT COUNSELING INFORMATION

Advise the patient to read the FDA-approved patient labeling (Medication Guide and Instructions for Use).

Acute Tubulointerstitial Nephritis

Advise the patient or caregiver to call the patient’s healthcare provider immediately if they experience signs and/or symptoms associated with acute tubulointerstitial nephritis [see Warnings and Precautions (5.2)].

Clostridium difficile-Associated Diarrhea

Advise the patient or caregiver to immediately call the patient’s healthcare provider if they experience diarrhea that does not improve [see Warnings and Precautions (5.3)].

Bone Fracture

Advise the patient or caregiver to report any fractures, especially of the hip, wrist or spine, to the patient’s healthcare provider [see Warnings and Precautions (5.4)].

Severe Cutaneous Adverse Reactions

Advise the patient or caregiver to discontinue PRILOSEC and report to their healthcare provider at the first appearance of a severe cutaneous adverse reaction or other sign of hypersensitivity [see Warnings and Precautions (5.5)].

Cutaneous and Systemic Lupus Erythematosus

Advise the patient or caregiver to immediately call the patient’s healthcare provider for any new or worsening of symptoms associated with cutaneous or systemic lupus erythematosus [see Warnings and Precautions (5.6)]

Cyanocobalamin (Vitamin B-12) Deficiency

Advise the patient or caregiver to report any clinical symptoms that may be associated with cyanocobalamin deficiency to the patient’s healthcare provider if they have been receiving PRILOSEC for longer than 3 years [see Warnings and Precautions (5.8)].

Hypomagnesemia and Mineral Metabolism

Advise the patient or caregiver to report any clinical symptoms that may be associated with hypomagnesemia, hypocalcemia, and/or hypokalemia to the patient’s healthcare provider, if they have been receiving PRILOSEC for at least 3 months [see Warnings and Precautions (5.9)].

Drug Interactions

Advise patients to report to their healthcare provider if they start treatment with rilpivirine-containing products, clopidogrel, St. John’s Wort or rifampin; or, if they take high-dose methotrexate [see Contraindications (4), Warnings and Precautions (5.7, 5.10, 5.12)].

Administration

- PRILOSEC is intended to be prepared in water and administered orally or via a nasogastric (NG) or gastric tube, as described in the Medication Guide.
- Take PRILOSEC before meals.
- Antacids may be used concomitantly with PRILOSEC.
- Missed doses: If a dose is missed, administer as soon as possible. However, if the next scheduled dose is due, do not take the missed dose, and take the next dose on time. Do not take two doses at one time to make up for a missed dose.

PRILOSEC is a trademark of the AstraZeneca group of companies. Manufactured for: Covis Pharma, Zug, 6300 Switzerland

©Covis Pharma 2024

MEDICATION GUIDE

PRILOSEC® (pry-lo-sec)
(omeprazole magnesium)
for delayed-release oral suspension

What is the most important information I should know about PRILOSEC?

PRILOSEC may help your acid-related symptoms, but you could still have serious stomach problems. Talk with your doctor.

PRILOSEC can cause serious side effects, including:

- A type of kidney problem (acute tubulointerstitial nephritis). Some people who take proton pump inhibitor (PPI) medicines, including PRILOSEC, may develop a kidney problem called acute tubulointerstitial nephritis that can happen at any time during treatment with PRILOSEC. Call your doctor right away if you have a decrease in the amount that you urinate or if you have blood in your urine.
- Diarrhea caused by an infection (Clostridium difficile) in your intestines. Call your doctor right away if you have watery stools or stomach pain that does not go away. You may or may not have a fever.
- Bone fractures (hip, wrist, or spine). Bone fractures in the hip, wrist, or spine may happen in people who take multiple daily doses of PPI medicines and for a long period of time (a year or longer). Tell your doctor if you have bone fracture especially in the hip, wrist, or spine.
- Certain types of lupus erythematosus. Lupus erythematosus is an autoimmune disorder (the body’s immune cells attack other cells or organs in the body). Some people who take PPI medicines, including PRILOSEC, may develop certain types of lupus erythematosus or have worsening of the lupus they already have. Call your doctor right away if you have new or worsening joint pain or a rash on your cheeks or arms that gets worse in the sun.

Talk to your doctor about your risk of these serious side effects.

PRILOSEC can have other serious side effects. See “What are the possible side effects of PRILOSEC?”

What is PRILOSEC?

A prescription medicine called a proton pump inhibitor (PPI) used to reduce the amount of acid in your stomach.

In adults, PRILOSEC is used for:

- for up to 8 weeks for the healing of duodenal ulcers.
- 10 to 14 days with certain antibiotics to treat an infection caused by bacteria called H. pylori. If needed, your doctor may prescribe another 14 to 18 days of PRILOSEC after treatment with the antibiotics.
- up to 8 weeks for the healing stomach ulcers.
- up to 4 weeks to treat heartburn and other symptoms that happen with gastroesophageal reflux disease (GERD).
- up to 8 weeks for the healing and symptom relief of acid-related damage to the lining of the esophagus (called erosive esophagitis or EE). Your doctor may prescribe another 4 weeks of PRILOSEC in patients whose EE does not heal.
- maintaining healing of EE and to help prevent the return of heartburn symptoms caused by GERD. It is not known if PRILOSEC is safe and effective when used for longer than 12 months for this purpose.
- the long-term treatment of conditions where your stomach makes too much acid. This includes a rare condition called Zollinger-Ellison Syndrome.

In children 1 to 16 years of age, PRILOSEC is used for:

- up to 4 weeks to treat heartburn and other symptoms that happen with GERD.
- up to 8 weeks to treat GERD with EE.
- maintaining healing of EE and to help prevent the return of heartburn symptoms caused by GERD. It is not known if PRILOSEC is safe and effective when used longer than 12 months for this purpose.

In children 1 month to less than 12 months of age, PRILOSEC is used for:

- up to 6 weeks to treat GERD with EE. It is not known if PRILOSEC is safe and effective for other uses in children 1 month to less than 12 months of age, or in children less than 1 month of age.

Do not take PRILOSEC if you are:

- allergic to omeprazole, any other PPI medicine, or any of the ingredients in PRILOSEC. See the end of this Medication Guide for a complete list of ingredients.
- taking a medicine that contains rilpivirine (EDURANT, COMPLERA, ODEFSEY) used to treat HIV-1 (Human Immunodeficiency Virus).

Before taking PRILOSEC, tell your doctor about all of your medical conditions, including if you:

- have low magnesium levels, low calcium levels and low potassium levels in your blood
- are pregnant or plan to become pregnant. It is not known if PRILOSEC will harm your unborn baby.
- are breastfeeding or plan to breastfeed. PRILOSEC can pass into your breast milk. Talk to your doctor about the best way to feed your baby if you take PRILOSEC.

Tell your doctor about all the medicines you take, including prescription and over-the-counter medicines, vitamins and herbal supplements. Especially tell your doctor if you take a medicine that contains clarithromycin or amoxicillin, clopidogrel (Plavix), methotrexate (Otrxup, Rasuvo, Trexall, XATMEP), digoxin (LANOXIN), a water pill (diuretic), St. John’s Wort (Hypericum perforatum), or rifampin (Rimactane, Rifater, Rifamate).

How should I take PRILOSEC?

- Take PRILOSEC exactly as prescribed by your doctor.
- Do not change your dose or stop PRILOSEC without talking to your doctor.
- PRILOSEC is usually taken 1 time each day.
- Take PRILOSEC before a meal.
- Antacids may be taken with PRILOSEC.
- PRILOSEC is mixed with water and can be taken by mouth, or given through a nasogastric (NG) tube or gastric tube.
- See the “Instructions for Use” at the end of this Medication Guide for instructions on how to mix and take PRILOSEC by mouth in water or how to mix and give PRILOSEC through an NG tube or gastric tube mixed in water.
- If you miss a dose of PRILOSEC, take it as soon as you remember. If it is almost time for your next dose, do not take the missed dose. Take the next dose at your regular time. Do not take 2 doses at the same time.
- If you take too much PRILOSEC, call your doctor or your poison control center at 1-800-222-1222 right away or go to the nearest emergency room.

What are the possible side effects of PRILOSEC?

PRILOSEC can cause serious side effects, including:

- See “What is the most important information I should know about PRILOSEC?”
- Low vitamin B-12 levels in your body can happen in people who have taken PRILOSEC for a long time (more than 3 years). Tell your doctor if you have symptoms of low vitamin B-12 levels, including shortness of breath, lightheadedness, irregular heartbeat, muscle weakness, pale skin, feeling tired, mood changes, and tingling or numbness in the arms and legs.
- Low magnesium levels and mineral metabolism in your body can happen in people who have taken PRILOSEC for at least 3 months. Tell your doctor if you have symptoms of low magnesium levels, including seizures, dizziness, irregular heartbeat, jitteriness, muscle aches or weakness, and spasms of hands, feet or voice.
- Stomach growths (fundic gland polyps). People who take PPI medicines for a long time have an increased risk of developing a certain type of stomach growths called fundic gland polyps, especially after taking PPI medicines for more than 1 year.
- Severe skin reactions. PRILOSEC can cause rare but severe skin reactions that may affect any part of your body. These serious skin reactions may need to be treated in a hospital and may be life threatening:
  - Skin rash which may have blistering, peeling or bleeding on any part of your skin (including your lips, eyes, mouth, nose, genitals, hands or feet).
  - You may also have fever, chills, body aches, shortness of breath, or enlarged lymph nodes.
Stop taking PRILOSEC and call your doctor right away. These symptoms may be the first sign of a severe skin reaction.

The most common side effects with PRILOSEC in adults include: headache, stomach-area (abdominal) pain, nausea, diarrhea, vomiting, and gas.

The most common side effects of PRILOSEC in children 1 to 16 years of age include: upper respiratory infection, fever, headache, stomach-area (abdominal) pain, nausea, diarrhea, vomiting, and gas.

These are not all the possible side effects of PRILOSEC. Call your doctor for medical advice about side effects. You may report side effects to FDA at 1-800-FDA-1088.

How should I store PRILOSEC?

Store PRILOSEC at room temperature between 68°F to 77°F (20°C to 25°C).

Keep PRILOSEC and all medicines out of the reach of children.

General information about the safe and effective use of PRILOSEC.

Medicines are sometimes prescribed for purposes other than those listed in a Medication Guide. Do not use PRILOSEC for a condition for which it was not prescribed. Do not give PRILOSEC to other people, even if they have the same symptoms that you have. It may harm them. You can ask your doctor or pharmacist for information about PRILOSEC that is written for health professionals.

What are the ingredients in PRILOSEC?

Active ingredient: omeprazole magnesium

Inactive ingredients: glyceryl monostearate, hydroxypropyl cellulose, hypromellose, magnesium stearate, methacrylic acid copolymer C, polysorbate, sugar spheres, talc, and triethyl citrate, and also inactive granules. The inactive granules are composed of citric acid, crospovidone, dextrose, hydroxypropyl cellulose, iron oxide and xanthan gum.

Manufactured for: Covis Pharma, Zug, 6300 Switzerland

PRILOSEC is a trademark of the AstraZeneca group of companies. ©2020 Covis Pharma. All rights reserved.

This Medication Guide has been approved by the U.S. Food and Drug Administration

Revised: March 2024

INSTRUCTIONS FOR USE

PRILOSEC® (pry-lo-sec)
(omeprazole magnesium)
for delayed-release oral suspension

Taking PRILOSEC in water:

1. PRILOSEC comes in packets containing 2.5 mg and 10 mg of PRILOSEC.
2. Use an oral syringe to draw up the amount of water needed to mix your dose. Ask your pharmacist for an oral syringe.
3. If your dose of PRILOSEC is 2.5 mg, add 5 mL of water to a clean container. Empty the contents of the 2.5 mg packet into the container of water.
4. If your dose of PRILOSEC is 10 mg, add 15 mL of water to a clean container. Empty the contents of the 10 mg packet into the container of water.
5. If you or your child are instructed to use more than 1 packet for your dose of PRILOSEC, follow the mixing instructions provided by your pharmacist or doctor.
6. Stir.
7. Leave the mixture for 2 to 3 minutes to thicken.
8. Stir and drink the mixture within 30 minutes. If not used within 30 minutes, throw away this dose and mix a new dose.
9. If any medicine remains after drinking, add more water, stir, and drink right away.

Giving PRILOSEC with water through a nasogastric (NG) tube or gastric tube:

For people who have an NG tube or gastric tube that is size 6 or larger, PRILOSEC may be given as follows:

1. PRILOSEC comes in packets containing 2.5 mg and 10 mg of PRILOSEC.
2. Use only a catheter tipped syringe to give PRILOSEC through an NG tube or gastric tube that is size 6 or larger.
3. If your dose of PRILOSEC is 2.5 mg, add 5 mL of water to a catheter tipped syringe. Add the contents of the 2.5 mg packet to the syringe.
4. If your dose of PRILOSEC is 10 mg, add 15 mL of water to a catheter tipped syringe. Add the contents of the 10 mg packet to the syringe.
5. Shake the syringe right away and then leave the mixture for 2 to 3 minutes to thicken.
6. Shake the syringe and inject through the NG tube or gastric tube into the stomach within 30 minutes.
7. Refill the syringe with the same amount of water you used to prepare your dose of PRILOSEC (5 mL or 15 mL of water depending on your dose).
8. Shake the syringe and flush any remaining medicine from the NG tube or gastric tube into the stomach.

PRINCIPAL DISPLAY PANEL - 2.5 mg Carton Label

2.5 mg Carton Label

NDC 70515-625-01

30 Single Dose
Packets

PRILOSEC®
(OMEPRAZOLE MAGNESIUM*)
FOR DELAYED-RELEASE
ORAL SUSPENSION

2.5 mg

Each carton contains 30 child-resistant packets.

*Each packet contains:
Omeprazole . . . . . . . . . 2.5 mg
(equivalent to 2.8 mg of omeprazole magnesium trihydrate)

Dispense the enclosed Medication Guide to each patient.

Rx only

COVIS

NDC 70515-625-01

PRILOSEC®
(OMEPRAZOLE MAGNESIUM*)
FOR DELAYED-RELEASE
ORAL SUSPENSION

2.5 mg

Store at 25°C (77°F); excursions permitted to 15-30°C (59-86°F). [See USP Controlled Room Temperature].
USUAL ADULT DOSAGE: See package insert.
PRILOSEC For Delayed-Release Oral Suspension should be administered as follows:
• Empty the contents of a 2.5 mg packet into a container containing 1 teaspoon (5 mL) of water
• Stir
• Leave 2 to 3 minutes to thicken
• Stir and drink within 30 minutes
• If any material remains after drinking, add more water, stir, and drink immediately

© Covis Pharma 2018
Manufactured for: Covis Pharma, Zug, 6300 Switzerland
Made in France

GTIN XXXXXXXXXXXXXX
LOT XXXXXXX
EXP MM-YYYY
SN XXXXXXXXXXXXXXXXXXXX

PRINCIPAL DISPLAY PANEL - 10 mg Carton Label

10 mg Carton Label

NDC 70515-610-01

30 Single Dose
Packets

PRILOSEC®
(OMEPRAZOLE MAGNESIUM*)
FOR DELAYED-RELEASE
ORAL SUSPENSION

10 mg

Each carton contains 30 child-resistant packets.

*Each packet contains:
Omeprazole . . . . . . . . . 10 mg
(equivalent to 11.2 mg of omeprazole magnesium trihydrate)

Dispense the enclosed Medication Guide to each patient.

Rx only

COVIS

NDC 70515-610-01

PRILOSEC®
(OMEPRAZOLE MAGNESIUM*)
FOR DELAYED-RELEASE
ORAL SUSPENSION

10 mg

Store at 25°C (77°F); excursions permitted to 15-30°C (59-86°F). [See USP Controlled Room Temperature].
USUAL ADULT DOSAGE: See package insert.

PRILOSEC For Delayed-Release Oral Suspension should be administered as follows:
• Empty the contents of a 10 mg packet into a container containing 1 tablespoon (15 mL) of water
• Stir
• Leave 2 to 3 minutes to thicken
• Stir and drink within 30 minutes
• If any material remains after drinking, add more water, stir, and drink immediately

© Covis Pharma 2018
Manufactured for: Covis Pharma, Zug, 6300 Switzerland
Made in France

GTIN XXXXXXXXXXXXXX
LOT XXXXXXX
EXP MM-YYYY
SN XXXXXXXXXXXXXXXXXXXX